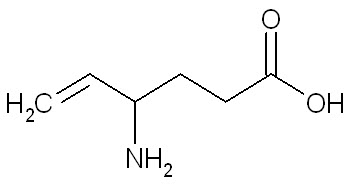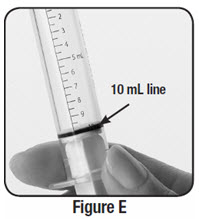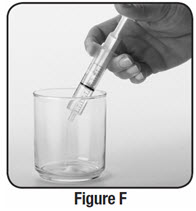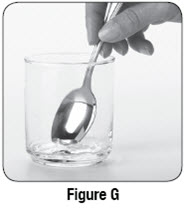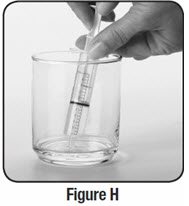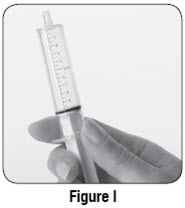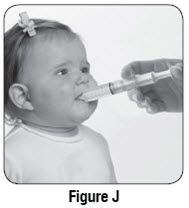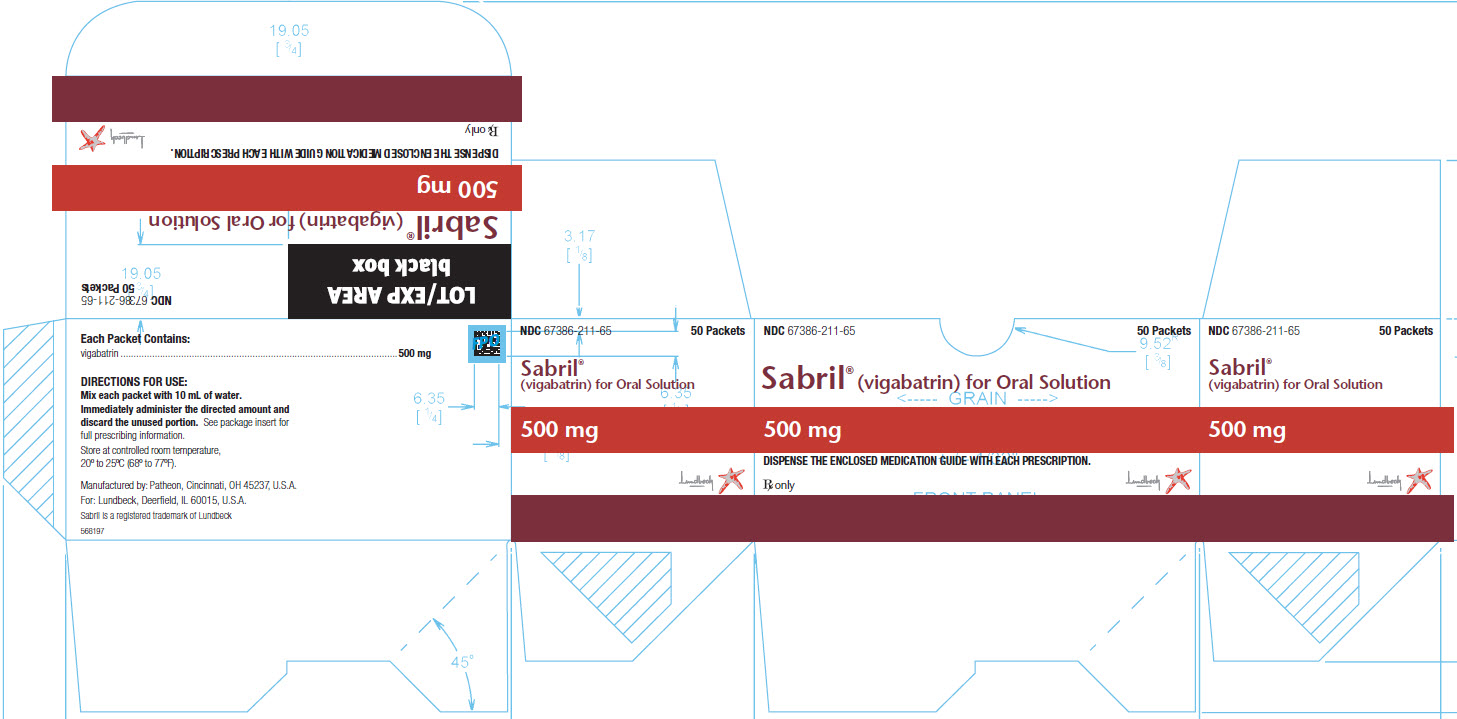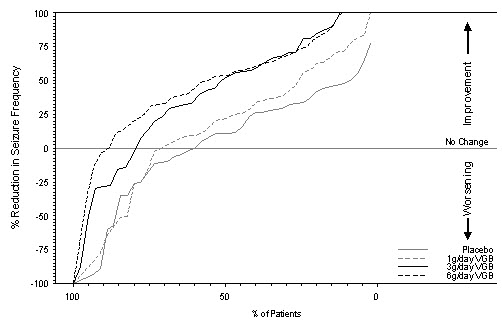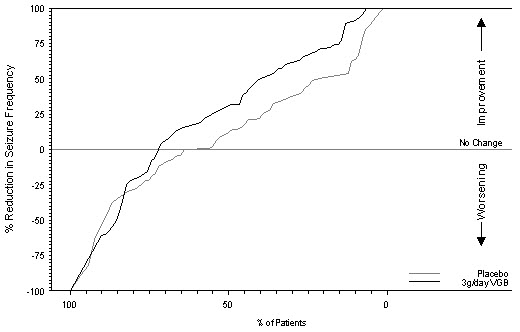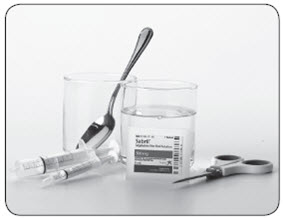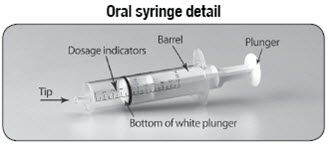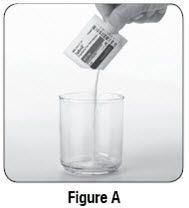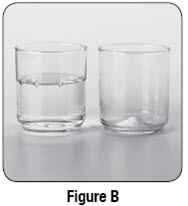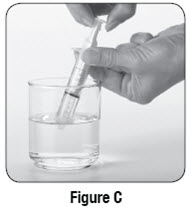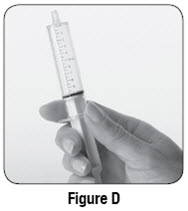 DRUG LABEL: SABRIL
NDC: 67386-211 | Form: POWDER, FOR SOLUTION
Manufacturer: Lundbeck Pharmaceuticals LLC
Category: prescription | Type: HUMAN PRESCRIPTION DRUG LABEL
Date: 20211020

ACTIVE INGREDIENTS: VIGABATRIN 50 mg/1 mL
INACTIVE INGREDIENTS: POVIDONE

HIGHLIGHTS OF PRESCRIBING INFORMATION

These highlights do not include all the information needed to use SABRIL safely and effectively. See full prescribing information for SABRIL.
SABRIL® (vigabatrin) tablets, for oral use
SABRIL® (vigabatrin) for oral solution
Initial U.S. Approval: 2009

WARNING: PERMANENT VISION LOSS

See full prescribing information for complete boxed warning.

- SABRIL can cause permanent bilateral concentric visual field constriction, including tunnel vision that can result in disability. In some cases, SABRIL may also decrease visual acuity (5.1).
- Risk increases with increasing dose and cumulative exposure, but there is no dose or exposure to SABRIL known to be free of risk of vision loss (5.1).
- Risk of new and worsening vision loss continues as long as SABRIL is used, and possibly after discontinuing SABRIL (5.1).
- Baseline and periodic vision assessment is recommended for patients on SABRIL. However, this assessment cannot always prevent vision damage (5.1).
- SABRIL is available only through a restricted program called the Vigabatrin REMS Program (5.2).

1 INDICATIONS AND USAGE

SABRIL is indicated for the treatment of:

- Refractory Complex Partial Seizures as adjunctive therapy in patients 2 years of age and older who have responded inadequately to several alternative treatments; SABRIL is not indicated as a first line agent (1.1)
- Infantile Spasms - monotherapy in infants 1 month to 2 years of age for whom the potential benefits outweigh the potential risk of vision loss (1.2)

2 DOSAGE AND ADMINISTRATION

Refractory Complex Partial Seizures

- Adults (17 years of age and older): Initiate at 1000 mg/day (500 mg twice daily); increase total daily dose weekly in 500 mg/day increments, to the recommended dose of 3000 mg/day (1500 mg twice daily) (2.2)
- Pediatric (2 to 16 years of age): The recommended dosage is based on body weight and administered as two divided doses (2.2)
- The dosage may be increased in weekly intervals, depending on response (2.2)
- Dose patients weighing more than 60 kg according to adult recommendations (2.2)

Infantile Spasms

- Initiate at a daily dose of 50 mg/kg (25 mg/kg twice daily); increase total daily dose every 3 days, in increments of 25 mg/kg/day to 50 mg/kg/day, up to a maximum daily dose of 150 mg/kg (75 mg/kg twice daily) (2.3)

Renal Impairment: Dose adjustment recommended (2.4, 8.5, 8.6)

3 DOSAGE FORMS AND STRENGTHS

- Tablet: 500 mg (3)
- For oral solution: 500 mg per packet (3)

4 CONTRAINDICATIONS

None (4)

5 WARNINGS AND PRECAUTIONS

- Abnormal MRI signal changes and intramyelinic edema have been reported in some infants with Infantile Spasms receiving SABRIL (5.3, 5.4)
- Suicidal behavior and ideation: Antiepileptic drugs, including SABRIL, increase the risk of suicidal thoughts and behavior (5.5)
- Withdrawal of AEDs: Taper dose to avoid withdrawal seizures (5.6)
- Anemia: Monitor for symptoms of anemia (5.7)
- Somnolence and fatigue: Advise patients not to drive or operate machinery until they have gained sufficient experience on SABRIL (5.8)

6 ADVERSE REACTIONS

Refractory Complex Partial Seizures

Most common adverse reactions in controlled studies include (incidence ≥5% over placebo):

- Adults: blurred vision, somnolence, dizziness, abnormal coordination, tremor, and fatigue (6.1)
- Pediatric patients (3 to 16 years of age): weight gain (6.1)

Infantile Spasms (incidence >5% and greater than on placebo)

- Somnolence, bronchitis, ear infection, and acute otitis media (6.1)

To report SUSPECTED ADVERSE REACTIONS, contact Lundbeck at 1-800-455-1141 or FDA at 1-800-FDA-1088 or www.fda.gov/medwatch.

7 DRUG INTERACTIONS

Decreased phenytoin plasma levels: dosage adjustment may be needed (7.1)

8 USE IN SPECIFIC POPULATIONS

- Pregnancy: Based on animal data, may cause fetal harm. (8.1)
- Lactation: SABRIL is excreted in human milk (8.2)

FULL PRESCRIBING INFORMATION

WARNING: PERMANENT VISION LOSS

- SABRIL can cause permanent bilateral concentric visual field constriction, including tunnel vision that can result in disability. In some cases, SABRIL also can damage the central retina and may decrease visual acuity [see Warnings and Precautions (5.1)].
- The onset of vision loss from SABRIL is unpredictable, and can occur within weeks of starting treatment or sooner, or at any time after starting treatment, even after months or years.
- Symptoms of vision loss from SABRIL are unlikely to be recognized by patients or caregivers before vision loss is severe. Vision loss of milder severity, while often unrecognized by the patient or caregiver, can still adversely affect function.
- The risk of vision loss increases with increasing dose and cumulative exposure, but there is no dose or exposure known to be free of risk of vision loss.
- Vision assessment is recommended at baseline (no later than 4 weeks after starting SABRIL), at least every 3 months during therapy, and about 3 to 6 months after the discontinuation of therapy.
- Once detected, vision loss due to SABRIL is not reversible. It is expected that, even with frequent monitoring, some patients will develop severe vision loss.
- Consider drug discontinuation, balancing benefit and risk, if visual loss is documented.
- Risk of new or worsening vision loss continues as long as SABRIL is used. It is possible that vision loss can worsen despite discontinuation of SABRIL.
- Because of the risk of visual loss, SABRIL should be withdrawn from patients with refractory complex partial seizures who fail to show substantial clinical benefit within 3 months of initiation and within 2-4 weeks of initiation for patients with infantile spasms, or sooner if treatment failure becomes obvious. Patient response to and continued need for SABRIL should be periodically reassessed.
- SABRIL should not be used in patients with, or at high risk of, other types of irreversible vision loss unless the benefits of treatment clearly outweigh the risks.
- SABRIL should not be used with other drugs associated with serious adverse ophthalmic effects such as retinopathy or glaucoma unless the benefits clearly outweigh the risks.
- Use the lowest dosage and shortest exposure to SABRIL consistent with clinical objectives [see Dosage and Administration (2.1)].

Because of the risk of permanent vision loss, SABRIL is available only through a restricted program under a Risk Evaluation and Mitigation Strategy (REMS) called the Vigabatrin REMS Program [see Warnings and Precautions (5.2)]. Further information is available at www.vigabatrinREMS.com or 1-866-244-8175.

1 INDICATIONS AND USAGE

1.1 Refractory Complex Partial Seizures (CPS)

SABRIL is indicated as adjunctive therapy for adults and pediatric patients 2 years of age and older with refractory complex partial seizures who have inadequately responded to several alternative treatments and for whom the potential benefits outweigh the risk of vision loss [see Warnings and Precautions (5.1)]. SABRIL is not indicated as a first line agent for complex partial seizures.

1.2 Infantile Spasms (IS)

SABRIL is indicated as monotherapy for pediatric patients with infantile spasms 1 month to 2 years of age for whom the potential benefits outweigh the potential risk of vision loss [see Warnings and Precautions (5.1)].

2 DOSAGE AND ADMINISTRATION

2.1 Important Dosing and Administration Instructions

Dosing

Use the lowest dosage and shortest exposure to SABRIL consistent with clinical objectives [see Warnings and Precautions (5.1)].

The SABRIL dosing regimen depends on the indication, age group, weight, and dosage form (tablets or for oral solution) [see Dosage and Administration (2.2, 2.3)]. Patients with impaired renal function require dose adjustment [see Dosage and Administration (2.4)].

Monitoring of SABRIL plasma concentrations to optimize therapy is not helpful.

Administration

SABRIL is given orally with or without food.

SABRIL for oral solution should be mixed with water prior to administration [see Dosage and Administration (2.5)]. A calibrated measuring device is recommended to measure and deliver the prescribed dose accurately. A household teaspoon or tablespoon is not an adequate measuring device.

If a decision is made to discontinue SABRIL, the dose should be gradually reduced [see Dosage and Administration (2.2, 2.3) and Warnings and Precautions (5.6)].

2.2 Refractory Complex Partial Seizures

Adults (Patients 17 Years of Age and Older)
Treatment should be initiated at 1000 mg/day (500 mg twice daily). Total daily dose may be increased in 500 mg increments at weekly intervals depending on response. The recommended dose of SABRIL in adults is 3000 mg/day (1500 mg twice daily). A 6000 mg/day dose has not been shown to confer additional benefit compared to the 3000 mg/day dose and is associated with an increased incidence of adverse events.

In controlled clinical studies in adults with complex partial seizures, SABRIL was tapered by decreasing the daily dose 1000 mg/day on a weekly basis until discontinued [see Warnings and Precautions (5.6)].

Pediatric (Patients 2 to 16 Years of Age)

The recommended dosage is based on body weight and administered as two divided doses, as shown in Table 1. The dosage may be increased in weekly intervals to the total daily maintenance dosage, depending on response.

Pediatric patients weighing more than 60 kg should be dosed according to adult recommendations.

Table 1. CPS Dosing Recommendations for Pediatric Patients Weighing 10 kg up to 60 kg††
Body Weight; [kg] | Total Daily*; Starting Dose; [mg/day] | Total Daily*; Maintenance Dose†; [mg/day]
10 kg to 15 kg | 350 mg | 1050 mg
Greater than 15 kg to 20 kg | 450 mg | 1300 mg
Greater than 20 kg to 25 kg | 500 mg | 1500 mg
Greater than 25 kg to 60 kg | 500 mg | 2000 mg
* Administered in two divided doses; † Maintenance dose is based on 3000 mg/day adult-equivalent dose; †† Patients weighing more than 60 kg should be dosed according to adult recommendations

In patients with refractory complex partial seizures, SABRIL should be withdrawn if a substantial clinical benefit is not observed within 3 months of initiating treatment. If, in the clinical judgment of the prescriber, evidence of treatment failure becomes obvious earlier than 3 months, treatment should be discontinued at that time [see Warnings and Precautions (5.1)].

In a controlled study in pediatric patients with complex partial seizures, SABRIL was tapered by decreasing the daily dose by one third every week for three weeks [see Warnings and Precautions (5.6)].

2.3 Infantile Spasms

The initial daily dosing is 50 mg/kg/day given in two divided doses (25 mg/kg twice daily); subsequent dosing can be titrated by 25 mg/kg/day to 50 mg/kg/day increments every 3 days, up to a maximum of 150 mg/kg/day given in 2 divided doses (75 mg/kg twice daily) [see Use in Specific Populations (8.4)].

Table 2 provides the volume of the 50 mg/mL dosing solution that should be administered as individual doses in infants of various weights.

Table 2. Infant Dosing Table
Weight [kg] | Starting Dose 50 mg/kg/day |  | Maximum Dose 150 mg/kg/day
3 | 1.5 mL twice daily |  | 4.5 mL twice daily
4 | 2 mL twice daily |  | 6 mL twice daily
5 | 2.5 mL twice daily |  | 7.5 mL twice daily
6 | 3 mL twice daily |  | 9 mL twice daily
7 | 3.5 mL twice daily |  | 10.5 mL twice daily
8 | 4 mL twice daily |  | 12 mL twice daily
9 | 4.5 mL twice daily |  | 13.5 mL twice daily
10 | 5 mL twice daily |  | 15 mL twice daily
11 | 5.5 mL twice daily |  | 16.5 mL twice daily
12 | 6 mL twice daily |  | 18 mL twice daily
13 | 6.5 mL twice daily |  | 19.5 mL twice daily
14 | 7 mL twice daily |  | 21 mL twice daily
15 | 7.5 mL twice daily |  | 22.5 mL twice daily
16 | 8 mL twice daily |  | 24 mL twice daily

In patients with infantile spasms, SABRIL should be withdrawn if a substantial clinical benefit is not observed within 2 to 4 weeks. If, in the clinical judgment of the prescriber, evidence of treatment failure becomes obvious earlier than 2 to 4 weeks, treatment should be discontinued at that time [see Warnings and Precautions (5.1)].

In a controlled clinical study in patients with infantile spasms, SABRIL was tapered by decreasing the daily dose at a rate of 25 mg/kg to 50 mg/kg every 3 to 4 days [see Warnings and Precautions (5.6)].

2.4 Patients with Renal Impairment

SABRIL is primarily eliminated through the kidney.

Infants
Information about how to adjust the dose in infants with renal impairment is unavailable.

Adult and pediatric patients 2 years and older

- Mild renal impairment (CLcr >50 to 80 mL/min): dose should be decreased by 25%
- Moderate renal impairment (CLcr >30 to 50 mL/min): dose should be decreased by 50%
- Severe renal impairment (CLcr >10 to 30 mL/min): dose should be decreased by 75%

CLcr in mL/min may be estimated from serum creatinine (mg/dL) using the following formulas:

- Patients 2 to <12 years old: CLcr (mL/min/1.73 m^2) = (K × Ht) / Scr

height (Ht) in cm; serum creatinine (Scr) in mg/dL
K (proportionality constant): Female Child (<12 years): K=0.55;
Male Child (<12 years): K=0.70

- Adult and pediatric patients 12 years or older: CLcr (mL/min) = [140-age (years)] × weight (kg) / [72 × serum creatinine (mg/dL)] (× 0.85 for female patients)

The effect of dialysis on SABRIL clearance has not been adequately studied [see Clinical Pharmacology (12.3) and Use in Specific Populations (8.6)].

2.5 Preparation and Administration Instructions for SABRIL for oral solution

If using SABRIL for oral solution, physicians should review and discuss the Medication Guide and instructions for mixing and giving SABRIL with the patient or caregiver(s). Physicians should confirm that patients or caregiver(s) understand how to mix SABRIL powder with water and administer the correct daily dose.

Empty the entire contents of each 500 mg packet into a clean cup, and dissolve in 10 mL of cold or room temperature water per packet. Administer the resulting solution using the 3 mL or 10 mL oral syringe provided by the pharmacy [see How Supplied/Storage and Handling (16.1)]. The concentration of the final solution is 50 mg/mL.

Table 3 below describes how many packets and how many milliliters (mL) of water will be needed to prepare each individual dose. The concentration after reconstitution is 50 mg/mL.

Table 3. Number of SABRIL Packets and mL of Water Needed for Each Individual Dose
Individual Dose [mg]; [Given Twice Daily] | Total Number of; SABRIL Packets | Total mL of Water; Required for Dissolving
0 to 500 | 1 Packet | 10 mL
501 to 1000 | 2 Packets | 20 mL
1001 to 1500 | 3 Packets | 30 mL

Discard the resulting solution if it is not clear (or free of particles) and colorless. Each individual dose should be prepared and used immediately. Discard any unused portion of the solution after administering the correct dose.

3 DOSAGE FORMS AND STRENGTHS

Tablet: 500 mg: white, oval, film-coated, biconvex, scored on one side, and debossed with OV 111 on the other.

For oral solution: 500 mg packet containing a white to off-white granular powder.

4 CONTRAINDICATIONS

None.

5 WARNINGS AND PRECAUTIONS

5.1 Permanent Vision Loss

SABRIL can cause permanent vision loss. Because of this risk and because, when it is effective, SABRIL provides an observable symptomatic benefit; patient response and continued need for treatment should be periodically assessed.

Based upon adult studies, 30 percent or more of patients can be affected with bilateral concentric visual field constriction ranging in severity from mild to severe. Severe cases may be characterized by tunnel vision to within 10 degrees of visual fixation, which can result in disability. In some cases, SABRIL also can damage the central retina and may decrease visual acuity. Symptoms of vision loss from SABRIL are unlikely to be recognized by patients or caregivers before vision loss is severe. Vision loss of milder severity, while often unrecognized by the patient or caregiver, can still adversely affect function.

Because assessing vision may be difficult in infants and children, the frequency and extent of vision loss is poorly characterized in these patients. For this reason, the understanding of the risk is primarily based on the adult experience. The possibility that vision loss from SABRIL may be more common, more severe, or have more severe functional consequences in infants and children than in adults cannot be excluded.

The onset of vision loss from SABRIL is unpredictable and can occur within weeks of starting treatment or sooner, or at any time after starting treatment, even after months or years.

The risk of vision loss increases with increasing dose and cumulative exposure, but there is no dose or exposure known to be free of risk of vision loss.

In patients with refractory complex partial seizures, SABRIL should be withdrawn if a substantial clinical benefit is not observed within 3 months of initiating treatment. If, in the clinical judgment of the prescriber, evidence of treatment failure becomes obvious earlier than 3 months, treatment should be discontinued at that time [see Dosage and Administration (2.2) and Warnings and Precautions (5.6)].

In patients with infantile spasms, SABRIL should be withdrawn if a substantial clinical benefit is not observed within 2 to 4 weeks. If, in the clinical judgment of the prescriber, evidence of treatment failure becomes obvious earlier than 2 to 4 weeks, treatment should be discontinued at that time [see Dosage and Administration (2.3) and Warnings and Precautions (5.6)].

SABRIL should not be used in patients with, or at high risk of, other types of irreversible vision loss unless the benefits of treatment clearly outweigh the risks. The interaction of other types of irreversible vision damage with vision damage from SABRIL has not been well-characterized, but is likely adverse.

SABRIL should not be used with other drugs associated with serious adverse ophthalmic effects such as retinopathy or glaucoma unless the benefits clearly outweigh the risks.

Monitoring of Vision

Monitoring of vision by an ophthalmic professional with expertise in visual field interpretation and the ability to perform dilated indirect ophthalmoscopy of the retina is recommended [see Warnings and Precautions (5.2)]. Because vision testing in infants is difficult, vision loss may not be detected until it is severe. For patients receiving SABRIL, vision assessment is recommended at baseline (no later than 4 weeks after starting SABRIL), at least every 3 months while on therapy, and about 3-6 months after the discontinuation of therapy. The diagnostic approach should be individualized for the patient and clinical situation.

In adults and cooperative pediatric patients, perimetry is recommended, preferably by automated threshold visual field testing. Additional testing may also include electrophysiology (e.g., electroretinography [ERG]), retinal imaging (e.g., optical coherence tomography [OCT]), and/or other methods appropriate for the patient. In patients who cannot be tested, treatment may continue according to clinical judgment, with appropriate patient counseling. Because of variability, results from ophthalmic monitoring must be interpreted with caution, and repeat assessment is recommended if results are abnormal or uninterpretable. Repeat assessment in the first few weeks of treatment is recommended to establish if, and to what degree, reproducible results can be obtained, and to guide selection of appropriate ongoing monitoring for the patient.

The onset and progression of vision loss from SABRIL is unpredictable, and it may occur or worsen precipitously between assessments. Once detected, vision loss due to SABRIL is not reversible. It is expected that even with frequent monitoring, some SABRIL patients will develop severe vision loss. Consider drug discontinuation, balancing benefit and risk, if vision loss is documented. It is possible that vision loss can worsen despite discontinuation of SABRIL.

5.2 Vigabatrin REMS Program

SABRIL is available only through a restricted distribution program called the Vigabatrin REMS Program, because of the risk of permanent vision loss.

Notable requirements of the Vigabatrin REMS Program include the following:

- Prescribers must be certified by enrolling in the program, agreeing to counsel patients on the risk of vision loss and the need for periodic monitoring of vision, and reporting any event suggestive of vision loss to Lundbeck.
- Patients must enroll in the program.
- Pharmacies must be certified and must only dispense to patients authorized to receive SABRIL.

Further information is available at www.vigabatrinREMS.com, or call 1-866-244-8175.

5.3 Magnetic Resonance Imaging (MRI) Abnormalities in Infants

Abnormal MRI signal changes characterized by increased T2 signal and restricted diffusion in a symmetric pattern involving the thalamus, basal ganglia, brain stem, and cerebellum have been observed in some infants treated with vigabatrin.

In a retrospective epidemiologic study in infants with infantile spasms (N=205), the prevalence of MRI changes was 22% in vigabatrin-treated patients versus 4% in patients treated with other therapies. In this study, in post marketing experience, and in published literature reports, these changes generally resolved with discontinuation of treatment. In a few patients, the lesion resolved despite continued use. It has been reported that some infants exhibited coincident motor abnormalities, but no causal relationship has been established and the potential for long-term clinical sequelae has not been adequately studied.

Neurotoxicity (brain histopathology and neurobehavioral abnormalities) was observed in rats exposed to vigabatrin during late gestation and the neonatal and juvenile periods of development, and brain histopathological changes were observed in dogs exposed to vigabatrin during the juvenile period of development. The relationship between these findings and the abnormal MRI findings in infants treated with vigabatrin for infantile spasms is unknown [see Warnings and Precautions (5.4) and Use in Specific Populations (8.1)].

The specific pattern of signal changes observed in patients 6 years and younger was not observed in older pediatric and adult patients treated with vigabatrin. In a blinded review of MRI images obtained in prospective clinical trials in patients with refractory complex partial seizures (CPS) 3 years and older (N=656), no difference was observed in anatomic distribution or prevalence of MRI signal changes between vigabatrin treated and placebo treated patients. In the postmarketing setting, MRI changes have also been reported in patients 6 years of age and younger being treated for refractory CPS.

For adults treated with SABRIL, routine MRI surveillance is unnecessary as there is no evidence that vigabatrin causes MRI changes in this population.

5.4 Neurotoxicity

Intramyelinic Edema (IME) has been reported in postmortem examination of infants being treated for infantile spasms with vigabatrin.

Abnormal MRI signal changes characterized by increased T2 signal and restricted diffusion in a symmetric pattern involving the thalamus, basal ganglia, brain stem, and cerebellum have also been observed in some infants treated for IS with vigabatrin. Studies of the effects of vigabatrin on MRI and evoked potentials (EP) in adult epilepsy patients have demonstrated no clear-cut abnormalities [see Warnings and Precautions (5.3)].

Vacuolation, characterized by fluid accumulation and separation of the outer layers of myelin, has been observed in brain white matter tracts in adult and juvenile rats and adult mice, dogs, and possibly monkeys following administration of vigabatrin. This lesion, referred to as intramyelinic edema (IME), was seen in animals at doses within the human therapeutic range. A no-effect dose was not established in rodents or dogs. In the rat and dog, vacuolation was reversible following discontinuation of vigabatrin treatment, but, in the rat, pathologic changes consisting of swollen or degenerating axons, mineralization, and gliosis were seen in brain areas in which vacuolation had been previously observed. Vacuolation in adult animals was correlated with alterations in MRI and changes in visual and somatosensory EP.

Administration of vigabatrin to rats during the neonatal and juvenile periods of development produced vacuolar changes in the brain gray matter (including the thalamus, midbrain, deep cerebellar nuclei, substantia nigra, hippocampus, and forebrain) which are considered distinct from the IME observed in vigabatrin treated adult animals. Decreased myelination and evidence of oligodendrocyte injury were additional findings in the brains of vigabatrin-treated rats. An increase in apoptosis was seen in some brain regions following vigabatrin exposure during the early postnatal period. Long-term neurobehavioral abnormalities (convulsions, neuromotor impairment, learning deficits) were also observed following vigabatrin treatment of young rats. Administration of vigabatrin to juvenile dogs produced vacuolar changes in the brain gray matter (including the septal nuclei, hippocampus, hypothalamus, thalamus, cerebellum, and globus pallidus). Neurobehavioral effects of vigabatrin were not assessed in the juvenile dog. These effects in young animals occurred at doses lower than those producing neurotoxicity in adult animals and were associated with plasma vigabatrin levels substantially lower than those achieved clinically in infants and children [see Use in Specific Populations (8.1, 8.4)].

In a published study, vigabatrin (200, 400 mg/kg/day) induced apoptotic neurodegeneration in the brain of young rats when administered by intraperitoneal injection on postnatal days 5-7.

Administration of vigabatrin to female rats during pregnancy and lactation at doses below those used clinically resulted in hippocampal vacuolation and convulsions in the mature offspring.

5.5 Suicidal Behavior and Ideation

Antiepileptic drugs (AEDs), including SABRIL, increase the risk of suicidal thoughts or behavior in patients taking these drugs for any indication. Patients treated with any AED for any indication should be monitored for the emergence or worsening of depression, suicidal thoughts or behavior, and/or any unusual changes in mood or behavior.

Pooled analyses of 199 placebo-controlled clinical trials (mono- and adjunctive therapy) of 11 different AEDs showed that patients randomized to one of the AEDs had approximately twice the risk (adjusted Relative Risk 1.8, 95% CI: 1.2, 2.7) of suicidal thinking or behavior compared to patients randomized to placebo. In these trials, which had a median treatment duration of 12 weeks, the estimated incidence rate of suicidal behavior or ideation among 27,863 AED treated patients was 0.43%, compared to 0.24% among 16,029 placebo-treated patients, representing an increase of approximately one case of suicidal thinking or behavior for every 530 patients treated. There were four suicides in drug treated patients in the trials and none in placebo treated patients, but the number is too small to allow any conclusion about drug effect on suicide.

The increased risk of suicidal thoughts or behavior with AEDs was observed as early as one week after starting drug treatment with AEDs and persisted for the duration of treatment assessed. Because most trials included in the analysis did not extend beyond 24 weeks, the risk of suicidal thoughts or behavior beyond 24 weeks could not be assessed.

The risk of suicidal thoughts or behavior was generally consistent among drugs in the data analyzed. The finding of increased risk with AEDs of varying mechanisms of action and across a range of indications suggests that the risk applies to all AEDs used for any indication. The risk did not vary substantially by age (5-100 years) in the clinical trials analyzed. Table 4 shows absolute and relative risk by indication for all evaluated AEDs.

Table 4. Risk by Indication for Antiepileptic Drugs in the Pooled Analysis
Indication | Placebo Patients with Events per 1000 Patients | Drug Patients with Events per 1000 Patients | Relative Risk: Incidence of Drug Events in Drug Patients/Incidence in Placebo Patients | Risk Difference: Additional Drug Patients with Events per 1000 Patients
Epilepsy | 1.0 | 3.4 | 3.5 | 2.4
Psychiatric | 5.7 | 8.5 | 1.5 | 2.9
Other | 1.0 | 1.8 | 1.9 | 0.9
Total | 2.4 | 4.3 | 1.8 | 1.9

The relative risk for suicidal thoughts or behavior was higher in clinical trials for epilepsy than in clinical trials for psychiatric or other conditions, but the absolute risk differences were similar for the epilepsy and psychiatric indications.

Anyone considering prescribing SABRIL or any other AED must balance the risk of suicidal thoughts or behavior with the risk of untreated illness. Epilepsy and many other illnesses for which AEDs are prescribed are themselves associated with morbidity and mortality and an increased risk of suicidal thoughts and behavior. Should suicidal thoughts and behavior emerge during treatment, the prescriber needs to consider whether the emergence of these symptoms in any given patient may be related to the illness being treated.

Patients, their caregivers, and families should be informed that AEDs increase the risk of suicidal thoughts and behavior and should be advised of the need to be alert for the emergence or worsening of the signs and symptoms of depression, any unusual changes in mood or behavior, or the emergence of suicidal thoughts, behavior, or thoughts about self-harm. Behaviors of concern should be reported immediately to healthcare providers.

5.6 Withdrawal of Antiepileptic Drugs (AEDs)

As with all AEDs, SABRIL should be withdrawn gradually. However, if withdrawal is needed because of a serious adverse event, rapid discontinuation can be considered. Patients and caregivers should be told not to suddenly discontinue SABRIL therapy.

In controlled clinical studies in adults with complex partial seizures, SABRIL was tapered by decreasing the daily dose 1000 mg/day on a weekly basis until discontinued.

In a controlled study in pediatric patients with complex partial seizures, SABRIL was tapered by decreasing the daily dose by one third every week for three weeks.

In a controlled clinical study in patients with infantile spasms, SABRIL was tapered by decreasing the daily dose at a rate of 25-50 mg/kg every 3-4 days.

5.7 Anemia

In North American controlled trials in adults, 6% of patients (16/280) receiving SABRIL and 2% of patients (3/188) receiving placebo had adverse events of anemia and/or met criteria for potentially clinically important hematology changes involving hemoglobin, hematocrit, and/or RBC indices. Across U.S. controlled trials, there were mean decreases in hemoglobin of about 3% and 0% in SABRIL and placebo-treated patients, respectively, and a mean decrease in hematocrit of about 1% in SABRIL-treated patients compared to a mean gain of about 1% in patients treated with placebo.

In controlled and open-label epilepsy trials in adults and pediatric patients, 3 SABRIL patients (0.06%, 3/4855) discontinued for anemia and 2 SABRIL patients experienced unexplained declines in hemoglobin to below 8 g/dL and/or hematocrit below 24%.

5.8 Somnolence and Fatigue

SABRIL causes somnolence and fatigue. Patients should be advised not to drive a car or operate other complex machinery until they are familiar with the effects of SABRIL on their ability to perform such activities.

Pooled data from two SABRIL controlled trials in adults demonstrated that 24% (54/222) of SABRIL patients experienced somnolence compared to 10% (14/135) of placebo patients. In those same studies, 28% of SABRIL patients experienced fatigue compared to 15% (20/135) of placebo patients. Almost 1% of SABRIL patients discontinued from clinical trials for somnolence and almost 1% discontinued for fatigue.

Pooled data from three SABRIL controlled trials in pediatric patients demonstrated that 6% (10/165) of SABRIL patients experienced somnolence compared to 5% (5/104) of placebo patients. In those same studies, 10% (17/165) of SABRIL patients experienced fatigue compared to 7% (7/104) of placebo patients. No SABRIL patients discontinued from clinical trials due to somnolence or fatigue.

5.9 Peripheral Neuropathy

SABRIL causes symptoms of peripheral neuropathy in adults. Pediatric clinical trials were not designed to assess symptoms of peripheral neuropathy, but observed incidence of symptoms based on pooled data from controlled pediatric studies appeared similar for pediatric patients on vigabatrin and placebo. In a pool of North American controlled and uncontrolled epilepsy studies, 4.2% (19/457) of SABRIL patients developed signs and/or symptoms of peripheral neuropathy. In the subset of North American placebo-controlled epilepsy trials, 1.4% (4/280) of SABRIL treated patients and no (0/188) placebo patients developed signs and/or symptoms of peripheral neuropathy. Initial manifestations of peripheral neuropathy in these trials included, in some combination, symptoms of numbness or tingling in the toes or feet, signs of reduced distal lower limb vibration or position sensation, or progressive loss of reflexes, starting at the ankles. Clinical studies in the development program were not designed to investigate peripheral neuropathy systematically and did not include nerve conduction studies, quantitative sensory testing, or skin or nerve biopsy. There is insufficient evidence to determine if development of these signs and symptoms was related to duration of SABRIL treatment, cumulative dose, or if the findings of peripheral neuropathy were completely reversible upon discontinuation of SABRIL.

5.10 Weight Gain

SABRIL causes weight gain in adult and pediatric patients.

Data pooled from randomized controlled trials in adults found that 17% (77/443) of SABRIL patients versus 8% (22/275) of placebo patients gained ≥7% of baseline body weight. In these same trials, the mean weight change among SABRIL patients was 3.5 kg compared to 1.6 kg for placebo patients.

Data pooled from randomized controlled trials in pediatric patients with refractory complex partial seizures found that 47% (77/163) of SABRIL patients versus 19% (19/102) of placebo patients gained ≥7% of baseline body weight.

In all epilepsy trials, 0.6% (31/4855) of SABRIL patients discontinued for weight gain. The long term effects of SABRIL related weight gain are not known. Weight gain was not related to the occurrence of edema.

5.11 Edema

SABRIL causes edema in adults. Pediatric clinical trials were not designed to assess edema, but observed incidence of edema-based pooled data from controlled pediatric studies appeared similar for pediatric patients on vigabatrin and placebo.

Pooled data from controlled trials demonstrated increased risk among SABRIL patients compared to placebo patients for peripheral edema (SABRIL 2%, placebo 1%), and edema (SABRIL 1%, placebo 0%). In these studies, one SABRIL and no placebo patients discontinued for an edema related AE. In adults, there was no apparent association between edema and cardiovascular adverse events such as hypertension or congestive heart failure. Edema was not associated with laboratory changes suggestive of deterioration in renal or hepatic function.

6 ADVERSE REACTIONS

The following serious and otherwise important adverse reactions are described elsewhere in labeling:

- Permanent Vision Loss [see BOXED WARNING and Warnings and Precautions (5.1)]
- Magnetic Resonance Imaging (MRI) Abnormalities in Infants [see Warnings and Precautions (5.3)]
- Neurotoxicity [see Warnings and Precautions (5.4)]
- Suicidal Behavior and Ideation [see Warnings and Precautions (5.5)]
- Withdrawal of Antiepileptic Drugs (AEDs) [see Warnings and Precautions (5.6)]
- Anemia [see Warnings and Precautions (5.7)]
- Somnolence and Fatigue [see Warnings and Precautions (5.8)]
- Peripheral Neuropathy [see Warnings and Precautions (5.9)]
- Weight Gain [see Warnings and Precautions (5.10)]
- Edema [see Warnings and Precautions (5.11)]

6.1 Clinical Trial Experience

Because clinical trials are conducted under widely varying conditions, adverse reaction rates observed in the clinical trials of a drug cannot be directly compared to rates in the clinical trials of another drug and may not reflect the rates observed in practice.

In U.S. and primary non-U.S. clinical studies of 4,079 SABRIL-treated patients, the most common (≥5%) adverse reactions associated with the use of SABRIL in combination with other AEDs were headache, somnolence, fatigue, dizziness, convulsion, nasopharyngitis, weight gain, upper respiratory tract infection, visual field defect, depression, tremor, nystagmus, nausea, diarrhea, memory impairment, insomnia, irritability, abnormal coordination, blurred vision, diplopia, vomiting, influenza, pyrexia, and rash.

The adverse reactions most commonly associated with SABRIL treatment discontinuation in ≥1% of patients were convulsion and depression.

In patients with infantile spasms, the adverse reactions most commonly associated with SABRIL treatment discontinuation in ≥1% of patients were infections, status epilepticus, developmental coordination disorder, dystonia, hypotonia, hypertonia, weight gain, and insomnia.

Refractory Complex Partial Seizures
Adults
Table 5 lists the adverse reactions that occurred in ≥2% and more than one patient per SABRIL-treated group and that occurred more frequently than in placebo patients from 2 U.S. adjunctive clinical studies of refractory CPS in adults.

Table 5. Adverse Reactions in Pooled, Adjunctive Trials in Adults with Refractory Complex Partial Seizures
 | SABRIL dosage (mg/day)
Body System Adverse Reaction | 3000 [N=134] % | 6000 [N=43] % | Placebo [N=135] %
Ear Disorders
Tinnitus | 2 | 0 | 1
Vertigo | 2 | 5 | 1
Eye Disorders
Blurred vision | 13 | 16 | 5
Diplopia | 7 | 16 | 3
Asthenopia | 2 | 2 | 0
Eye pain | 0 | 5 | 0
Gastrointestinal Disorders
Diarrhea | 10 | 16 | 7
Nausea | 10 | 2 | 8
Vomiting | 7 | 9 | 6
Constipation | 8 | 5 | 3
Upper abdominal pain | 5 | 5 | 1
Dyspepsia | 4 | 5 | 3
Stomach discomfort | 4 | 2 | 1
Abdominal pain | 3 | 2 | 1
Toothache | 2 | 5 | 2
Abdominal distension | 2 | 0 | 1
General Disorders
Fatigue | 23 | 40 | 16
Gait disturbance | 6 | 12 | 7
Asthenia | 5 | 7 | 1
Edema peripheral | 5 | 7 | 1
Fever | 4 | 7 | 3
Chest pain | 1 | 5 | 1
Thirst | 2 | 0 | 0
Malaise | 0 | 5 | 0
Infections
Nasopharyngitis | 14 | 9 | 10
Upper respiratory tract infection | 7 | 9 | 6
Influenza | 5 | 7 | 4
Urinary tract infection | 4 | 5 | 0
Bronchitis | 0 | 5 | 1
Injury
Contusion | 3 | 5 | 2
Joint sprain | 1 | 2 | 1
Muscle strain | 1 | 2 | 1
Wound secretion | 0 | 2 | 0
Metabolism and Nutrition Disorders
Increased appetite | 1 | 5 | 1
Weight gain | 6 | 14 | 3
Musculoskeletal Disorders
Arthralgia | 10 | 5 | 3
Back pain | 4 | 7 | 2
Pain in extremity | 6 | 2 | 4
Myalgia | 3 | 5 | 1
Muscle twitching | 1 | 9 | 1
Muscle spasms | 3 | 0 | 1
Nervous System Disorders
Headache | 33 | 26 | 31
Somnolence | 22 | 26 | 13
Dizziness | 24 | 26 | 17
Nystagmus | 13 | 19 | 9
Tremor | 15 | 16 | 8
Memory impairment | 7 | 16 | 3
Abnormal coordination | 7 | 16 | 2
Disturbance in attention | 9 | 0 | 1
Sensory disturbance | 4 | 7 | 2
Hyporeflexia | 4 | 5 | 1
Paraesthesia | 7 | 2 | 1
Lethargy | 4 | 7 | 2
Hyperreflexia | 4 | 2 | 3
Hypoaesthesia | 4 | 5 | 1
Sedation | 4 | 0 | 0
Status epilepticus | 2 | 5 | 0
Dysarthria | 2 | 2 | 1
Postictal state | 2 | 0 | 1
Sensory loss | 0 | 5 | 0
Psychiatric Disorders
Irritability | 7 | 23 | 7
Depression | 6 | 14 | 3
Confusional state | 4 | 14 | 1
Anxiety | 4 | 0 | 3
Depressed mood | 5 | 0 | 1
Abnormal thinking | 3 | 7 | 0
Abnormal behavior | 3 | 5 | 1
Expressive language disorder | 1 | 7 | 1
Nervousness | 2 | 5 | 2
Abnormal dreams | 1 | 5 | 1
Reproductive System
Dysmenorrhea | 9 | 5 | 3
Erectile dysfunction | 0 | 5 | 0
Respiratory and Thoracic Disorders
Pharyngolaryngeal pain | 7 | 14 | 5
Cough | 2 | 14 | 7
Pulmonary congestion | 0 | 5 | 1
Sinus headache | 6 | 2 | 1
Skin and Subcutaneous Tissue Disorders
Rash | 4 | 5 | 4

Pediatrics 2 to 16 years of age
Table 6 lists adverse reactions from controlled clinical studies of pediatric patients receiving SABRIL or placebo as adjunctive therapy for refractory complex partial seizures. Adverse reactions that are listed occurred in at least 2% of SABRIL-treated patients and more frequently than placebo. The median SABRIL dose was 49.4 mg/kg (range of 8.0 – 105.9 mg/kg).

Table 6. Adverse Reactions in Pooled, Adjunctive Trials in Pediatric Patients 3 to 16 Years of Age with Refractory Complex Partial Seizures
Body System; Adverse Reaction | All SABRIL [N=165] % | Placebo [N=104] %
Eye Disorders
Diplopia | 3 | 2
Blurred vision | 2 | 0
Gastrointestinal Disorders
Upper abdominal pain | 4 | 3
Constipation | 2 | 1
General Disorders
Fatigue | 10 | 7
Infections and Infestations
Upper respiratory tract infection | 15 | 11
Influenza | 7 | 3
Otitis media | 6 | 4
Streptococcal pharyngitis | 4 | 3
Viral gastroenteritis | 2 | 0
Investigations
Weight gain | 15 | 2
Nervous System Disorders
Somnolence | 6 | 5
Nystagmus | 4 | 3
Tremor | 4 | 2
Status epilepticus | 2 | 1
Psychiatric Disorders
Abnormal behavior | 7 | 6
Aggression | 6 | 2
Disorientation | 3 | 0

Safety of SABRIL for the treatment of refractory CPS in patients 2 years of age is expected to be similar to pediatric patients 3 to 16 years of age.

Infantile Spasms
In a randomized, placebo-controlled IS study with a 5 day double-blind treatment phase (n=40), the adverse reactions that occurred in >5% of patients receiving SABRIL and that occurred more frequently than in placebo patients were somnolence (SABRIL 45%, placebo 30%), bronchitis (SABRIL 30%, placebo 15%), ear infection (SABRIL 10%, placebo 5%), and acute otitis media (SABRIL 10%, placebo 0%).

In a dose response study of low-dose (18-36 mg/kg/day) versus high-dose (100-148 mg/kg/day) SABRIL, no clear correlation between dose and incidence of adverse reactions was observed. The adverse reactions (≥5% in either dose group) are summarized in Table 7.

Table 7. Adverse Reactions in a Placebo-Controlled Trial in Patients with Infantile Spasms
 | SABRIL Low Dose | SABRIL High Dose
Body System Adverse Reaction | [N=114] % | [N=108] %
Eye Disorders (other than field or acuity changes)
Strabismus | 5 | 5
Conjunctivitis | 5 | 2
Gastrointestinal Disorders
Vomiting | 14 | 20
Constipation | 14 | 12
Diarrhea | 13 | 12
General Disorders
Fever | 29 | 19
Infections
Upper respiratory tract infection | 51 | 46
Otitis media | 44 | 30
Viral infection | 20 | 19
Pneumonia | 13 | 11
Candidiasis | 8 | 3
Ear infection | 7 | 14
Gastroenteritis viral | 6 | 5
Sinusitis | 5 | 9
Urinary tract infection | 5 | 6
Influenza | 5 | 3
Croup infectious | 5 | 1
Metabolism & Nutrition Disorders
Decreased appetite | 9 | 7
Nervous System Disorders
Sedation | 19 | 17
Somnolence | 17 | 19
Status epilepticus | 6 | 4
Lethargy | 5 | 7
Convulsion | 4 | 7
Hypotonia | 4 | 6
Psychiatric Disorders
Irritability | 16 | 23
Insomnia | 10 | 12
Respiratory Disorders
Nasal congestion | 13 | 4
Cough | 3 | 8
Skin and Subcutaneous Tissue Disorders
Rash | 8 | 11

6.2 Postmarketing Experience

The following adverse reactions have been identified during postapproval use of SABRIL. Because these reactions are reported voluntarily from a population of uncertain size, it is not always possible to reliably estimate their frequency or establish a causal relationship to drug exposure. Adverse reactions are categorized by system organ class.

Birth Defects: Congenital cardiac defects, congenital external ear anomaly, congenital hemangioma, congenital hydronephrosis, congenital male genital malformation, congenital oral malformation, congenital vesicoureteric reflux, dentofacial anomaly, dysmorphism, fetal anticonvulsant syndrome, hamartomas, hip dysplasia, limb malformation, limb reduction defect, low set ears, renal aplasia, retinitis pigmentosa, supernumerary nipple, talipes

Ear Disorders: Deafness

Endocrine Disorders: Delayed puberty

Gastrointestinal Disorders: Gastrointestinal hemorrhage, esophagitis

General Disorders: Developmental delay, facial edema, malignant hyperthermia, multi-organ failure

Hepatobiliary Disorders: Cholestasis

Nervous System Disorders: Dystonia, encephalopathy, hypertonia, hypotonia, muscle spasticity, myoclonus, optic neuritis, dyskinesia

Psychiatric Disorders: Acute psychosis, apathy, delirium, hypomania, neonatal agitation, psychotic disorder

Respiratory Disorders: Laryngeal edema, pulmonary embolism, respiratory failure, stridor

Skin and Subcutaneous Tissue Disorders: Angioedema, maculo-papular rash, pruritus, Stevens-Johnson syndrome (SJS), toxic epidermal necrolysis (TEN), alopecia

7 DRUG INTERACTIONS

7.1 Antiepileptic Drugs

Phenytoin
Although phenytoin dose adjustments are not routinely required, dose adjustment of phenytoin should be considered if clinically indicated, since SABRIL may cause a moderate reduction in total phenytoin plasma levels [see Clinical Pharmacology (12.3)].

Clonazepam
SABRIL may moderately increase the Cmax of clonazepam resulting in an increase of clonazepam-associated adverse reactions [see Clinical Pharmacology (12.3)].

Other AEDs
There are no clinically significant pharmacokinetic interactions between SABRIL and either phenobarbital or sodium valproate. Based on population pharmacokinetics, carbamazepine, clorazepate, primidone, and sodium valproate appear to have no effect on plasma concentrations of vigabatrin [see Clinical Pharmacology (12.3)].

7.2 Oral Contraceptives

SABRIL is unlikely to affect the efficacy of steroid oral contraceptives [see Clinical Pharmacology (12.3)].

7.3 Drug-Laboratory Test Interactions

SABRIL decreases alanine transaminase (ALT) and aspartate transaminase (AST) plasma activity in up to 90% of patients. In some patients, these enzymes become undetectable. The suppression of ALT and AST activity by SABRIL may preclude the use of these markers, especially ALT, to detect early hepatic injury.

SABRIL may increase the amount of amino acids in the urine, possibly leading to a false positive test for certain rare genetic metabolic diseases (e.g., alpha aminoadipic aciduria).

8 USE IN SPECIFIC POPULATIONS

8.1 Pregnancy

Pregnancy Exposure Registry

There is a pregnancy exposure registry that monitors pregnancy outcomes in women exposed to AEDs, including SABRIL, during pregnancy. Encourage women who are taking SABRIL during pregnancy to enroll in the North American Antiepileptic Drug (NAAED) Pregnancy Registry. This can be done by calling the toll-free number 1-888-233-2334 or visiting the website, http://www.aedpregnancyregistry.org/. This must be done by the patient herself.

Risk Summary

There are no adequate data on the developmental risk associated with the use of SABRIL in pregnant women. Limited available data from case reports and cohort studies pertaining to SABRIL use in pregnant women have not established a drug-associated risk of major birth defects, miscarriage, or adverse maternal or fetal outcomes. However, based on animal data, SABRIL use in pregnant women may result in fetal harm.

When administered to pregnant animals, vigabatrin produced developmental toxicity, including an increase in fetal malformations and offspring neurobehavioral and neurohistopathological effects, at clinically relevant doses. In addition, developmental neurotoxicity was observed in rats treated with vigabatrin during a period of postnatal development corresponding to the third trimester of human pregnancy (see Data).

In the U.S. general population, the estimated background risk of major birth defects and miscarriage in clinically recognized pregnancies is 2-4% and 15-20%, respectively. The background risk of major birth defects and miscarriage for the indicated population is unknown.

Data

Animal Data

Administration of vigabatrin (oral doses of 50 to 200 mg/kg/day) to pregnant rabbits throughout the period of organogenesis was associated with an increased incidence of malformations (cleft palate) and embryofetal death; these findings were observed in two separate studies. The no-effect dose for adverse effects on embryofetal development in rabbits (100 mg/kg/day) is approximately 1/2 the maximum recommended human dose (MRHD) of 3 g/day on a body surface area (mg/m^2) basis. In rats, oral administration of vigabatrin (50, 100, or 150 mg/kg/day) throughout organogenesis resulted in decreased fetal body weights and increased incidences of fetal anatomic variations. The no-effect dose for adverse effects on embryo-fetal development in rats (50 mg/kg/day) is approximately 1/5 the MRHD on a mg/m^2 basis. Oral administration of vigabatrin (50, 100, 150 mg/kg/day) to rats from the latter part of pregnancy through weaning produced long-term neurohistopathological (hippocampal vacuolation) and neurobehavioral (convulsions) abnormalities in the offspring. A no-effect dose for developmental neurotoxicity in rats was not established; the low-effect dose (50 mg/kg/day) is approximately 1/5 the MRHD on a mg/m^2 basis.

In a published study, vigabatrin (300 or 450 mg/kg) was administered by intraperitoneal injection to a mutant mouse strain on a single day during organogenesis (day 7, 8, 9, 10, 11, or 12). An increase in fetal malformations (including cleft palate) was observed at both doses.

Oral administration of vigabatrin (5, 15, or 50 mg/kg/day) to young rats during the neonatal and juvenile periods of development (postnatal days 4-65) produced neurobehavioral (convulsions, neuromotor impairment, learning deficits) and neurohistopathological (brain vacuolation, decreased myelination, and retinal dysplasia) abnormalities in treated animals. The early postnatal period in rats is generally thought to correspond to late pregnancy in humans in terms of brain development. The no-effect dose for developmental neurotoxicity in juvenile rats (5 mg/kg/day) was associated with plasma vigabatrin exposures (AUC) less than 1/30 of those measured in pediatric patients receiving an oral dose of 50 mg/kg.

8.2 Lactation

Risk Summary

Vigabatrin is excreted in human milk. The effects of SABRIL on the breastfed infant and on milk production are unknown. Because of the potential for serious adverse reactions from vigabatrin in nursing infants, breastfeeding is not recommended. If exposing a breastfed infant to SABRIL, observe for any potential adverse effects [see Warnings and Precautions (5.1, 5.3, 5.4, 5.8)].

8.4 Pediatric Use

The safety and effectiveness of SABRIL as adjunctive treatment of refractory complex partial seizures in pediatric patients 2 to 16 years of age have been established and is supported by three double-blind, placebo-controlled studies in patients 3 to 16 years of age, adequate and well-controlled studies in adult patients, pharmacokinetic data from patients 2 years of age and older, and additional safety information in patients 2 years of age [see Clinical Pharmacology (12.3) and Clinical Studies (14.1)]. The dosing recommendation in this population varies according to age group and is weight-based [see Dosage and Administration (2.2)]. Adverse reactions in this pediatric population are similar to those observed in the adult population [see Adverse Reactions (6.1)]. The safety and effectiveness of SABRIL as monotherapy for pediatric patients with infantile spasms (1 month to 2 years of age) have been established [see Dosage and Administration (2.3) and Clinical Studies (14.2)].

Safety and effectiveness as adjunctive treatment of refractory complex partial seizures in pediatric patients below the age of 2 and as monotherapy for the treatment of infantile spasms in pediatric patients below the age of 1 month have not been established.

Duration of therapy for infantile spasms was evaluated in a post hoc analysis of a Canadian Pediatric Epilepsy Network (CPEN) study of developmental outcomes in infantile spasms patients. This analysis suggests that a total duration of 6 months of vigabatrin therapy is adequate for the treatment of infantile spasms. However, prescribers must use their clinical judgment as to the most appropriate duration of use [see Clinical Studies (14.2)].

Abnormal MRI signal changes and Intramyelinic Edema (IME) in infants and young children being treated with SABRIL have been observed [see Warnings and Precautions (5.3, 5.4)].

Juvenile Animal Toxicity Data

Oral administration of vigabatrin (5, 15, or 50 mg/kg/day) to young rats during the neonatal and juvenile periods of development (postnatal days 4-65) produced neurobehavioral (convulsions, neuromotor impairment, learning deficits) and neurohistopathological (brain gray matter vacuolation, decreased myelination, and retinal dysplasia) abnormalities. The no-effect dose for developmental neurotoxicity in juvenile rats (the lowest dose tested) was associated with plasma vigabatrin exposures (AUC) substantially less than those measured in pediatric patients at recommended doses. In dogs, oral administration of vigabatrin (30 or 100 mg/kg/day) during selected periods of juvenile development (postnatal days 22-112) produced neurohistopathological abnormalities (brain gray matter vacuolation). Neurobehavioral effects of vigabatrin were not assessed in the juvenile dog. A no-effect dose for neurohistopathology was not established in juvenile dogs; the lowest effect dose (30 mg/kg/day) was associated with plasma vigabatrin exposures lower than those measured in pediatric patients at recommended doses [see Warnings and Precautions (5.4)].

8.5 Geriatric Use

Clinical studies of vigabatrin did not include sufficient numbers of patients aged 65 and over to determine whether they responded differently from younger patients.

Vigabatrin is known to be substantially excreted by the kidney, and the risk of toxic reactions to this drug may be greater in patients with impaired renal function. Because elderly patients are more likely to have decreased renal function, care should be taken in dose selection, and it may be useful to monitor renal function.

Oral administration of a single dose of 1.5 g of vigabatrin to elderly (≥65 years) patients with reduced creatinine clearance (<50 mL/min) was associated with moderate to severe sedation and confusion in 4 of 5 patients, lasting up to 5 days. The renal clearance of vigabatrin was 36% lower in healthy elderly subjects (≥65 years) than in young healthy males. Adjustment of dose or frequency of administration should be considered. Such patients may respond to a lower maintenance dose [see Dosage and Administration (2.4) and Clinical Pharmacology (12.3)].

Other reported clinical experience has not identified differences in responses between the elderly and younger patients.

8.6 Renal Impairment

Dose adjustment, including initiating treatment with a lower dose, is necessary in pediatric patients 2 years of age and older and adults with mild (creatinine clearance >50 to 80 mL/min), moderate (creatinine clearance >30 to 50 mL/min) and severe (creatinine clearance >10 to 30 mL/min) renal impairment [see Dosage and Administration (2.4) and Clinical Pharmacology (12.3)].

9 DRUG ABUSE AND DEPENDENCE

9.1 Controlled Substance

Vigabatrin is not a controlled substance.

9.2 Abuse

Vigabatrin did not produce adverse events or overt behaviors associated with abuse when administered to humans or animals. It is not possible to predict the extent to which a CNS active drug will be misused, diverted, and/or abused once marketed. Consequently, physicians should carefully evaluate patients for history of drug abuse and follow such patients closely, observing them for signs of misuse or abuse of vigabatrin (e.g., incrementation of dose, drug-seeking behavior).

9.3 Dependence

Following chronic administration of vigabatrin to animals, there were no apparent withdrawal signs upon drug discontinuation. However, as with all AEDs, vigabatrin should be withdrawn gradually to minimize increased seizure frequency [see Warnings and Precautions (5.6)].

10 OVERDOSAGE

10.1 Signs, Symptoms, and Laboratory Findings of Overdosage

Confirmed and/or suspected vigabatrin overdoses have been reported during clinical trials and in post marketing surveillance. No vigabatrin overdoses resulted in death. When reported, the vigabatrin dose ingested ranged from 3 g to 90 g, but most were between 7.5 g and 30 g. Nearly half the cases involved multiple drug ingestions including carbamazepine, barbiturates, benzodiazepines, lamotrigine, valproic acid, acetaminophen, and/or chlorpheniramine.

Coma, unconsciousness, and/or drowsiness were described in the majority of cases of vigabatrin overdose. Other less commonly reported symptoms included vertigo, psychosis, apnea or respiratory depression, bradycardia, agitation, irritability, confusion, headache, hypotension, abnormal behavior, increased seizure activity, status epilepticus, and speech disorder. These symptoms resolved with supportive care.

10.2 Management of Overdosage

There is no specific antidote for SABRIL overdose. Standard measures to remove unabsorbed drug should be used, including elimination by emesis or gastric lavage. Supportive measures should be employed, including monitoring of vital signs and observation of the clinical status of the patient.

In an in vitro study, activated charcoal did not significantly adsorb vigabatrin.

The effectiveness of hemodialysis in the treatment of SABRIL overdose is unknown. In isolated case reports in renal failure patients receiving therapeutic doses of vigabatrin, hemodialysis reduced vigabatrin plasma concentrations by 40% to 60%.

11 DESCRIPTION

SABRIL (vigabatrin) is an oral antiepileptic drug and is available as white film-coated 500 mg tablets and as a white to off-white granular powder for oral solution in packets of 500 mg.

The chemical name of vigabatrin, a racemate consisting of two enantiomers, is (±) 4-amino-5-hexenoic acid. The molecular formula is C6H11NO2 and the molecular weight is 129.16. It has the following structural formula:

Vigabatrin is a white to off-white powder which is freely soluble in water, slightly soluble in methyl alcohol, very slightly soluble in ethyl alcohol and chloroform, and insoluble in toluene and hexane. The pH of a 1% aqueous solution is about 6.9. The n-octanol/water partition coefficient of vigabatrin is about 0.011 (log P=-1.96) at physiologic pH. Vigabatrin melts with decomposition in a 3-degree range within the temperature interval of 171ºC to 176ºC. The dissociation constants (pKa) of vigabatrin are 4 and 9.7 at room temperature (25ºC).

Each SABRIL tablet contains 500 mg of vigabatrin. The inactive ingredients are hydroxypropyl methylcellulose, magnesium stearate, microcrystalline cellulose, polyethylene glycols, povidone, sodium starch glycolate, and titanium dioxide.

SABRIL for oral solution is available as a white to off-white granular powder. Each packet contains 500 mg of vigabatrin. The inactive ingredient is povidone.

12 CLINICAL PHARMACOLOGY

12.1 Mechanism of Action

The precise mechanism of vigabatrin’s anti-seizure effect is unknown, but it is believed to be the result of its action as an irreversible inhibitor of γ-aminobutyric acid transaminase (GABA-T), the enzyme responsible for the metabolism of the inhibitory neurotransmitter GABA. This action results in increased levels of GABA in the central nervous system.

No direct correlation between plasma concentration and efficacy has been established. The duration of drug effect is presumed to be dependent on the rate of enzyme re-synthesis rather than on the rate of elimination of the drug from the systemic circulation.

12.2 Pharmacodynamics

Effects on Electrocardiogram
There is no indication of a QT/QTc prolonging effect of SABRIL in single doses up to 6.0 g. In a randomized, placebo-controlled, crossover study, 58 healthy subjects were administered a single oral dose of SABRIL (3 g and 6 g) and placebo. Peak concentrations for 6.0 g SABRIL were approximately 2-fold higher than the peak concentrations following the 3.0 g single oral dose.

12.3 Pharmacokinetics

Vigabatrin displayed linear pharmacokinetics after administration of single doses ranging from 0.5 g to 4 g, and after administration of repeated doses of 0.5 g and 2.0 g twice daily. Bioequivalence has been established between the oral solution and tablet formulations. The following PK information (Tmax, half-life, and clearance) of vigabatrin was obtained from stand-alone PK studies and population PK analyses.

Absorption
Following oral administration, vigabatrin is essentially completely absorbed. The time to maximum concentration (Tmax) is approximately 1 hour for children and adolescents (3 years to 16 years of age) and adults, and approximately 2.5 hours for infants (5 months to 2 years of age). There was little accumulation with multiple dosing in adult and pediatric patients. A food effect study involving administration of vigabatrin to healthy volunteers under fasting and fed conditions indicated that the Cmax was decreased by 33%, Tmax was increased to 2 hours, and AUC was unchanged under fed conditions.

Distribution
Vigabatrin does not bind to plasma proteins. Vigabatrin is widely distributed throughout the body; mean steady-state volume of distribution is 1.1 L/kg (CV = 20%).

Metabolism and Elimination
Vigabatrin is not significantly metabolized; it is eliminated primarily through renal excretion. The terminal half-life of vigabatrin is about 5.7 hours for infants (5 months to 2 years of age), 6.8 hours for children (3 to 9 years of age), 9.5 hours for children and adolescents (10 to 16 years of age), and 10.5 hours for adults. Following administration of [14]C-vigabatrin to healthy male volunteers, about 95% of total radioactivity was recovered in the urine over 72 hours with the parent drug representing about 80% of this. Vigabatrin induces CYP2C9, but does not induce other hepatic cytochrome P450 enzyme systems.

Specific Populations

Geriatric
The renal clearance of vigabatrin in healthy elderly patients (≥65 years of age) was 36% less than those in healthy younger patients. This finding is confirmed by an analysis of data from a controlled clinical trial [see Use in Specific Populations (8.5)].

Pediatric
The clearance of vigabatrin is 2.4 L/hr for infants (5 months to 2 years of age), 5.1 L/hr for children (3 to 9 years of age), 5.8 L/hr for children and adolescents (10 to 16 years of age) and 7 L/hr for adults.

Gender
No gender differences were observed for the pharmacokinetic parameters of vigabatrin in patients.

Race
No specific study was conducted to investigate the effects of race on vigabatrin pharmacokinetics. A cross study comparison between 23 Caucasian and 7 Japanese patients who received 1, 2, and 4 g of vigabatrin indicated that the AUC, Cmax, and half-life were similar for the two populations. However, the mean renal clearance of Caucasians (5.2 L/hr) was about 25% higher than the Japanese (4.0 L/hr). Inter-subject variability in renal clearance was 20% in Caucasians and was 30% in Japanese.

Renal Impairment
Mean AUC increased by 30% and the terminal half-life increased by 55% (8.1 hr vs 12.5 hr) in adult patients with mild renal impairment (CLcr from >50 to 80 mL/min) in comparison to normal subjects.

Mean AUC increased by two-fold and the terminal half-life increased by two-fold in adult patients with moderate renal impairment (CLcr from >30 to 50 mL/min) in comparison to normal subjects.

Mean AUC increased by 4.5-fold and the terminal half-life increased by 3.5-fold in adult patients with severe renal impairment (CLcr from >10 to 30 mL/min) in comparison to normal subjects.

Adult patients with renal impairment
Dosage adjustment, including starting at a lower dose, is recommended for adult patients with any degree of renal impairment [see Use in Specific Populations (8.6) and Dosage and Administration (2.4)].

Infants with renal impairment
Information about how to adjust the dose in infants with renal impairment is unavailable.

Pediatric patients 2 years and older with renal impairment
Although information is unavailable on the effects of renal impairment on vigabatrin clearance in pediatric patients 2 years and older, dosing can be calculated based upon adult data and an established formula [see Use in Specific Populations (8.6) and Dosage and Administration (2.4)].

Hepatic Impairment
Vigabatrin is not significantly metabolized. The pharmacokinetics of vigabatrin in patients with impaired liver function has not been studied.

Drug Interactions

Phenytoin
A 16% to 20% average reduction in total phenytoin plasma levels was reported in adult controlled clinical studies. In vitro drug metabolism studies indicate that decreased phenytoin concentrations upon addition of vigabatrin therapy are likely to be the result of induction of cytochrome P450 2C enzymes in some patients. Although phenytoin dose adjustments are not routinely required, dose adjustment of phenytoin should be considered if clinically indicated [see Drug Interactions (7.1)].

Clonazepam
In a study of 12 healthy adult volunteers, clonazepam (0.5 mg) co-administration had no effect on SABRIL (1.5 g twice daily) concentrations. SABRIL increases the mean Cmax of clonazepam by 30% and decreases the mean Tmax by 45% [see Drug Interactions (7.1)].

Other AEDs
When co-administered with vigabatrin, phenobarbital concentration (from phenobarbital or primidone) was reduced by an average of 8% to 16%, and sodium valproate plasma concentrations were reduced by an average of 8%. These reductions did not appear to be clinically relevant. Based on population pharmacokinetics, carbamazepine, clorazepate, primidone, and sodium valproate appear to have no effect on plasma concentrations of vigabatrin [see Drug Interactions (7.1)].

Alcohol
Co-administration of ethanol (0.6 g/kg) with vigabatrin (1.5 g twice daily) indicated that neither drug influences the pharmacokinetics of the other.

Oral Contraceptives
In a double-blind, placebo-controlled study using a combination oral contraceptive containing 30 mcg ethinyl estradiol and 150 mcg levonorgestrel, vigabatrin (3 g/day) did not interfere significantly with the cytochrome P450 isoenzyme (CYP3A)-mediated metabolism of the contraceptive tested. Based on this study, vigabatrin is unlikely to affect the efficacy of steroid oral contraceptives. Additionally, no significant difference in pharmacokinetic parameters (elimination half-life, AUC, Cmax, apparent oral clearance, time to peak, and apparent volume of distribution) of vigabatrin were found after treatment with ethinyl estradiol and levonorgestrel [see Drug Interactions (7.2)].

13 NONCLINICAL TOXICOLOGY

13.1 Carcinogenesis, Mutagenesis, Impairment of Fertility

Vigabatrin showed no carcinogenic potential in mouse or rat when given in the diet at doses up to 150 mg/kg/day for 18 months (mouse) or at doses up to 150 mg/kg/day for 2 years (rat). These doses are less than the maximum recommended human dose (MRHD) for infantile spasms (150 mg/kg/day) and for refractory complex partial seizures (3 g/day) on a mg/m^2 basis.

Vigabatrin was negative in in vitro (Ames, CHO/HGPRT mammalian cell forward gene mutation, chromosomal aberration in rat lymphocytes) and in in vivo (mouse bone marrow micronucleus) assays.

No adverse effects on male or female fertility were observed in rats at oral doses up to 150 mg/kg/day (approximately 1/2 the MRHD of 3 g/day on a mg/m^2 basis for refractory complex partial seizures).

14 CLINICAL STUDIES

14.1 Complex Partial Seizures

Adults

The effectiveness of SABRIL as adjunctive therapy in adult patients was established in two U.S. multicenter, double-blind, placebo-controlled, parallel-group clinical studies. A total of 357 adults (age 18 to 60 years) with complex partial seizures, with or without secondary generalization were enrolled (Studies 1 and 2). Patients were required to be on an adequate and stable dose of an anticonvulsant, and have a history of failure on an adequate regimen of carbamazepine or phenytoin. Patients had a history of about 8 seizures per month (median) for about 20 years (median) prior to entrance into the study. These studies were not capable by design of demonstrating direct superiority of SABRIL over any other anticonvulsant added to a regimen to which the patient had not adequately responded. Further, in these studies patients had previously been treated with a limited range of anticonvulsants.

The primary measure of efficacy was the patient’s reduction in mean monthly frequency of complex partial seizures plus partial seizures secondarily generalized at end of study compared to baseline.

Study 1

Study 1 (N=174) was a randomized, double-blind, placebo-controlled, dose-response study consisting of an 8-week baseline period followed by an 18-week treatment period. Patients were randomized to receive placebo or 1, 3, or 6 g/day vigabatrin administered twice daily. During the first 6 weeks following randomization, the dose was titrated upward beginning with 1 g/day and increasing by 0.5 g/day on days 1 and 5 of each subsequent week in the 3 g/day and 6 g/day groups, until the assigned dose was reached.

Results for the primary measure of effectiveness, reduction in monthly frequency of complex partial seizures, are shown in Table 8. The 3 g/day and 6 g/day dose groups were statistically significantly superior to placebo, but the 6 g/day dose was not superior to the 3 g/day dose.

Table 8. Median Monthly Frequency of Complex Partial Seizures^+
 | N | Baseline | Endstudy
Placebo | 45 | 9.0 | 8.8
1 g/day SABRIL | 45 | 8.5 | 7.7
3 g/day SABRIL | 41 | 8.5 | 3.7*
6 g/day SABRIL | 43 | 8.5 | 4.5*
*p<0.05 compared to placebo
^+Including one patient with simple partial seizures with secondary generalization only

Figure 1 presents the percentage of patients (X-axis) with a percent reduction in seizure frequency (responder rate) from baseline to the maintenance phase at least as great as that represented on the Y-axis. A positive value on the Y-axis indicates an improvement from baseline (i.e., a decrease in complex partial seizure frequency), while a negative value indicates a worsening from baseline (i.e., an increase in complex partial seizure frequency). Thus, in a display of this type, a curve for an effective treatment is shifted to the left of the curve for placebo. The proportion of patients achieving any particular level of reduction in complex partial seizure frequency was consistently higher for the SABRIL 3 and 6 g/day groups compared to the placebo group. For example, 51% of patients randomized to SABRIL 3 g/day and 53% of patients randomized to SABRIL 6 g/day experienced a 50% or greater reduction in seizure frequency, compared to 9% of patients randomized to placebo. Patients with an increase in seizure frequency >100% are represented on the Y-axis as equal to or greater than -100%.

Figure 1. Percent Reduction from Baseline in Seizure Frequency

Study 2

Study 2 (N=183 randomized, 182 evaluated for efficacy) was a randomized, double-blind, placebo-controlled, parallel study consisting of an 8-week baseline period and a 16-week treatment period. During the first 4 weeks following randomization, the dose of vigabatrin was titrated upward beginning with 1 g/day and increased by 0.5 g/day on a weekly basis to the maintenance dose of 3 g/day.

Results for the primary measure of effectiveness, reduction in monthly complex partial seizure frequency, are shown in Table 9. Vigabatrin 3 g/day was statistically significantly superior to placebo in reducing seizure frequency.

Table 9. Median Monthly Frequency of Complex Partial Seizures
 | N | Baseline | Endstudy
Placebo | 90 | 9.0 | 7.5
3 g/day SABRIL | 92 | 8.3 | 5.5*
*p<0.05 compared to placebo

Figure 2 presents the percentage of patients (X-axis) with a percent reduction in seizure frequency (responder rate) from baseline to the maintenance phase at least as great as that represented on the Y-axis. A positive value on the Y-axis indicates an improvement from baseline (i.e., a decrease in complex partial seizure frequency), while a negative value indicates a worsening from baseline (i.e., an increase in complex partial seizure frequency). Thus, in a display of this type, a curve for an effective treatment is shifted to the left of the curve for placebo. The proportion of patients achieving any particular level of reduction in seizure frequency was consistently higher for the SABRIL 3 g/day group compared to the placebo group. For example, 39% of patients randomized to SABRIL (3 g/day) experienced a 50% or greater reduction in complex partial seizure frequency, compared to 21% of patients randomized to placebo. Patients with an increase in seizure frequency >100% are represented on the Y-axis as equal to or greater than -100%.

Figure 2. Percent Reduction from Baseline in Seizure Frequency

For both studies, there was no difference in the effectiveness of vigabatrin between male and female patients. Analyses of age and race were not possible as nearly all patients were between the ages of 18 to 65 and Caucasian.

Pediatric patients 3 to 16 years of age

SABRIL was studied in three double-blind, placebo-controlled, parallel-group studies in 269 patients who received SABRIL and 104 patients who received placebo. No individual study was considered adequately powered to determine efficacy in pediatric patients age 3 years and above. The data from all three pediatric studies were pooled and used in a pharmacometric bridging analysis using weight-normalized doses to establish efficacy and determine appropriate dosing. All three studies were randomized, double-blind, placebo-controlled, parallel-group, adjunctive-treatment studies in patients aged 3-16 years with uncontrolled complex partial seizures with or without secondary generalization. The study period included a 6 to 10 week baseline phase and a 14 to 17 week treatment phase (composed of a titration and maintenance period).

The pharmacometric bridging approach consisted of defining a weight-normalized dose-response, and showing that a similar dose-response relationship exists between pediatric patients and adults patients when SABRIL was given as adjunctive therapy for complex partial seizures. Dosing recommendations in pediatric patients 2 to 16 years of age were derived from simulations utilizing these pharmacometric dose-response analyses [see Dosage and Administration (2.2)].

14.2 Infantile Spasms

The effectiveness of SABRIL as monotherapy was established for infantile spasms in two multicenter controlled studies. Both studies were similar in terms of disease characteristics and prior treatments of patients and all enrolled infants had a confirmed diagnosis of infantile spasms.

Study 1

Study 1 (N=221) was a multicenter, randomized, low-dose high-dose, parallel-group, partially-blind (caregivers knew the actual dose but not whether their child was classified as low or high dose; EEG reader was blinded but investigators were not blinded) study to evaluate the safety and efficacy of vigabatrin in patients <2 years of age with new-onset infantile spasms. Patients with both symptomatic and cryptogenic etiologies were studied. The study was comprised of two phases. The first phase was a 14 to 21 day partially-blind phase in which patients were randomized to receive either low-dose (18-36 mg/kg/day) or high-dose (100-148 mg/kg/day) vigabatrin. Study drug was titrated over 7 days, followed by a constant dose for 7 days. If the patient became spasm-free on or before day 14, another 7 days of constant dose was administered. The primary efficacy endpoint of this study was the proportion of patients who were spasm-free for 7 consecutive days beginning within the first 14 days of vigabatrin therapy. Patients considered spasm-free were defined as those patients who remained free of spasms (evaluated according to caregiver response to direct questioning regarding spasm frequency) and who had no indication of spasms or hypsarrhythmia during 8 hours of CCTV EEG recording (including at least one sleep-wake-sleep cycle) performed within 3 days of the seventh day of spasm freedom and interpreted by a blinded EEG reader. Seventeen patients in the high-dose group achieved spasm freedom compared with 8 patients in the low dose group. This difference was statistically significant (p=0.0375). Primary efficacy results are shown in Table 10.

Table 10. Spasm Freedom by Primary Criteria (Study 1)
 |  | SABRIL Treatment Group
 |  | 18-36 mg/kg/day [N=114] n (%) | 100-148 mg/kg/day [N=107] n (%)
Patients who Achieved Spasm Freedom |  | 8 (7.0) | 17 (15.9)
p=0.0375
Note: Primary criteria were evaluated based on caregiver assessment plus CCTV EEG confirmation within 3 days of the seventh day of spasm freedom.

Study 2

Study 2 (N=40) was a multicenter, randomized, double-blind, placebo-controlled, parallel-group study consisting of a pre-treatment (baseline) period of 2-3 days, followed by a 5-day double-blind treatment phase during which patients were treated with vigabatrin (initial dose of 50 mg/kg/day with titration allowed to 150 mg/kg/day) or placebo. The primary efficacy endpoint in this study was the average percent change in daily spasm frequency, assessed during a pre-defined and consistent 2-hour window of evaluation, comparing baseline to the final 2 days of the 5-day double-blind treatment phase. No statistically significant differences were observed in the average frequency of spasms using the 2-hour evaluation window. However, a post-hoc alternative efficacy analysis, using a 24-hour clinical evaluation window found a statistically significant difference in the overall percentage of reductions in spasms between the vigabatrin group (68.9%) and the placebo group (17.0%) (p=0.030).

Duration of therapy for infantile spasms was evaluated in a post hoc analysis of a Canadian Pediatric Epilepsy Network (CPEN) study of developmental outcomes in infantile spasms patients. The 38/68 infants in the study who had responded to vigabatrin therapy (complete cessation of spasms and hypsarrhythmia) continued vigabatrin therapy for a total duration of 6 months therapy. The 38 infants who responded were then followed for an additional 18 months after discontinuation of vigabatrin to determine their clinical outcome. A post hoc analysis indicated no observed recurrence of infantile spasms in any of these 38 infants.

16 HOW SUPPLIED/STORAGE AND HANDLING

16.1 How Supplied

SABRIL 500 mg tablets are white, film-coated, oval, biconvex, scored on one side, and debossed with OV 111 on the other. They are supplied as bottles of 100 (NDC 67386-111-01).

SABRIL for oral solution is available as 500 mg packets containing a white to off-white granular powder. They are supplied in packages of 50 (NDC 67386-211-65).

The oral syringes are provided separately by the pharmacy.

16.2 Storage and Handling

Store at 20°C to 25°C (68°F to 77°F). See USP controlled room temperature.

17 PATIENT COUNSELING INFORMATION

Advise patients and caregivers to read the FDA-approved patient labeling (Medication Guide and Instructions for Use).

Administration Instructions for SABRIL for oral solution

Physicians should confirm that caregivers(s) understand how to mix SABRIL for oral solution and to administer the correct dose to their infants and pediatric patients [see Dosage and Administration (2.5)].

Permanent Vision Loss
Inform patients and caregivers of the risk of permanent vision loss, particularly loss of peripheral vision, from SABRIL, and the need for monitoring vision [see Warnings and Precautions (5.1)].

Monitoring of vision, including assessment of visual fields and visual acuity, is recommended at baseline (no later than 4 weeks after starting SABRIL), at least every 3 months while on therapy, and about 3-6 months after discontinuation of therapy. In patients for whom vision testing is not possible, treatment may continue without recommended testing according to clinical judgment with appropriate patient or caregiver counseling. Patients or caregivers should be informed that if baseline or subsequent vision is not normal, SABRIL should only be used if the benefits of SABRIL treatment clearly outweigh the risks of additional vision loss.

Advise patients and caregivers that vision testing may be insensitive and may not detect vision loss before it is severe. Also advise patients and caregivers that if vision loss is documented, such loss is irreversible. Ensure that both of these points are understood by patients and caregivers.

Patients and caregivers should be informed that if changes in vision are suspected, they should notify their physician immediately.

Vigabatrin REMS Program
SABRIL is available only through a restricted program called the Vigabatrin REMS Program [see Warnings and Precautions (5.2)]. Inform patients/caregivers of the following:

- Patients/caregivers must be enrolled in the program.
- SABRIL is only available through pharmacies that are enrolled in the Vigabatrin REMS Program.

MRI Abnormalities in Infants
Inform caregiver(s) of the possibility that infants may develop an abnormal MRI signal of unknown clinical significance [see Warnings and Precautions (5.3)].

Suicidal Thinking and Behavior
Counsel patients, their caregiver(s), and families that AEDs, including SABRIL, may increase the risk of suicidal thoughts and behavior. Also advise patients and caregivers of the need to be alert for the emergence or worsening of symptoms of depression, any unusual changes in mood or behavior, or the emergence of suicidal thoughts, behavior, or thoughts of self-harm. Behaviors of concern should be reported immediately to healthcare providers [see Warnings and Precautions (5.5)].

Pregnancy

Advise pregnant women and women of child-bearing potential that the use of SABRIL during pregnancy can cause fetal harm which may occur early in pregnancy before many women know they are pregnant. Instruct patients to notify their physician if they become pregnant or intend to become pregnant during therapy. Advise patients that there is a pregnancy exposure registry that collects information about the safety of antiepileptic drugs during pregnancy [see Use in Specific Populations (8.1)].

Nursing

Counsel patients that SABRIL is excreted in breast milk. Because of the potential for serious adverse reactions in nursing infants from SABRIL, breastfeeding is not recommended. If a decision is made to breastfeed, nursing mothers should be counseled to observe their infants for signs of vision loss, sedation and poor sucking [see Use in Specific Populations (8.2)].

Withdrawal of SABRIL Therapy
Instruct patients and caregivers not to suddenly discontinue SABRIL therapy without consulting with their healthcare provider. As with all AEDs, withdrawal should be gradual [see Warnings and Precautions (5.6)].

Manufactured by: Patheon
Cincinnati, OH 45237, U.S.A.

For: Lundbeck
Deerfield, IL 60015, U.S.A.

SABRIL is a registered trademark of Lundbeck

MEDICATION GUIDE

SABRIL® (SAY-bril)
(vigabatrin)
Tablets

SABRIL® (SAY-bril)
(vigabatrin)
for oral solution

What is the most important information I should know about SABRIL?

SABRIL can cause serious side effects, including:

- Permanent vision loss
- Magnetic resonance imaging (MRI) changes in babies with infantile spasms (IS)
- Risk of suicidal thoughts or actions

1. Permanent vision loss:

SABRIL can damage the vision of anyone who takes it. Some people can have severe loss particularly to their ability to see to the side when they look straight ahead (peripheral vision). With severe vision loss, you may only be able to see things straight in front of you (sometimes called “tunnel vision”). You may also have blurry vision. If this happens, it will not get better.

- Vision loss and use of SABRIL in adults and children 2 years and older: Because of the risk of vision loss, SABRIL is used to treat complex partial seizures (CPS) only in people who do not respond well enough to several other medicines.

Tell your healthcare provider right away if you (or your child):

- might not be seeing as well as before starting SABRIL.
- start to trip, bump into things, or are more clumsy than usual.
- are surprised by people or things coming in front of you that seem to come out of nowhere.

- These changes can mean that you (or your child) have damage to your vision.
- It is recommended that your healthcare provider test your (or your child’s) vision (including peripheral vision) and visual acuity (ability to read an eye chart) before you (or your child) start SABRIL or within 4 weeks after starting SABRIL, and at least every 3 months after that until SABRIL is stopped. It is also recommended that you (or your child) have a vision test about 3 to 6 months after SABRIL is stopped. Your vision loss may get worse after you stop taking Sabril.
- Some people are not able to complete testing of vision. Your healthcare provider will determine if you (or your child) can be tested. If you (or your child) cannot complete vision testing, your healthcare provider may continue prescribing SABRIL, but your healthcare provider will not be able to watch for any vision loss you (or your child) may get.
- Even if your vision (or your child’s vision) seems fine, it is important that you (or your child) get these regular vision tests because vision damage can happen before you (or your child) notice any changes.
- These vision tests cannot prevent the vision damage that can happen with SABRIL, but they do allow the healthcare provider to decide if you (or your child) should stop SABRIL if your vision has gotten worse.
- Vision testing may not detect vision loss before it is severe.
- If you do not have these vision tests regularly, your healthcare provider may stop prescribing SABRIL.
- If you drive and your vision is damaged by SABRIL, driving might be more dangerous, or you may not be able to drive safely at all. Talk about this with your healthcare provider.
- Vision loss in babies: Because of the risk of vision loss, SABRIL is used in babies 1 month to 2 years of age with infantile spasms (IS) only when you and your healthcare provider decide that the possible benefits of SABRIL are more important than the risks.

- Parents or caregivers are not likely to recognize the symptoms of vision loss in babies until it is severe. Healthcare providers may not find vision loss in babies until it is severe.
- It is difficult to test vision in babies, but, to the extent possible, all babies should have their vision tested before starting SABRIL or within 4 weeks after starting SABRIL, and every 3 months after that until SABRIL is stopped. Your baby should also have a vision test about 3 to 6 months after SABRIL is stopped.
- Your baby may not be able to be tested. Your healthcare provider will determine if your baby can be tested. If your baby cannot be tested, your healthcare provider may continue prescribing SABRIL, but your healthcare provider will not be able to watch for any vision loss.

Tell your healthcare provider right away if you think that your baby is:

- not seeing as well as before taking SABRIL.
- acting differently than normal.

- Even if your baby’s vision seems fine, it is important to get regular vision tests because damage can happen before your baby acts differently. Even these regular vision exams may not show the damage to your baby’s vision before it is severe and permanent.

All people who take SABRIL:

- You are at risk for permanent vision loss with any amount of SABRIL.
- Your risk of vision loss may be higher the more SABRIL you take daily and the longer you take it.
- It is not possible for your healthcare provider to know when vision loss will happen. It could happen soon after starting SABRIL or any time during treatment. It may even happen after treatment has stopped.

- Because SABRIL might cause permanent vision loss, it is available to healthcare providers and patients only under a special program called the Vigabatrin Risk Evaluation and Mitigation Strategy (REMS) Program. SABRIL can only be prescribed to people who are enrolled in this program. As part of the Vigabatrin REMS Program, it is recommended that your healthcare provider test your (or your child’s) vision from time to time (periodically) while you (or your child) are being treated with SABRIL, and even after you (or your child) stop treatment. Your healthcare provider will explain the details of the Vigabatrin REMS Program to you. For more information, go to www.vigabatrinREMS.com or call 1-866-244-8175.

2. Magnetic resonance imaging (MRI) changes in babies with infantile spasms:

Brain pictures taken by magnetic resonance imaging (MRI) show changes in some babies after they are given SABRIL. It is not known if these changes are harmful.

3. Risk of suicidal thoughts or actions:

Like other antiepileptic drugs, SABRIL may cause suicidal thoughts or actions in a very small number of people, about 1 in 500 people taking it. Call a healthcare provider right away if you or your child have any of these symptoms, especially if they are new, worse, or worry you:

- thoughts about suicide or dying
- attempts to commit suicide
- new or worse depression
- new or worse anxiety
- feeling agitated or restless
- panic attacks
- trouble sleeping (insomnia)
- new or worse irritability
- acting aggressive, being angry, or violent
- acting on dangerous impulses
- an extreme increase in activity and talking (mania)
- other unusual changes in behavior or mood

Suicidal thoughts or actions can be caused by things other than medicines. If you or your child have suicidal thoughts or actions, your healthcare provider may check for other causes.

How can I watch for early symptoms of suicidal thoughts and actions?

- Pay attention to any changes, especially sudden changes, in mood, behaviors, thoughts, or feelings.
- Keep all follow-up visits with your healthcare provider as scheduled.
- Call your healthcare provider between visits as needed, especially if you are worried about symptoms.
- Do not stop SABRIL without first talking to a healthcare provider.
- Stopping SABRIL suddenly can cause serious problems. Stopping a seizure medicine suddenly can cause seizures that will not stop (status epilepticus) in people who are being treated for seizures.

What is SABRIL?

- SABRIL is a prescription medicine used along with other treatments to treat adults and children 2 years and older with complex partial seizures (CPS) if:
  ○ the CPS do not respond well enough to several other treatments, and
  ○ you and your healthcare provider decide the possible benefit of taking SABRIL is more important than the risk of vision loss.
  SABRIL should not be the first medicine used to treat CPS.

- SABRIL is also used to treat babies 1 month to 2 years of age who have infantile spasms (IS) if you and your healthcare provider decide the possible benefits of taking SABRIL are more important than the possible risk of vision loss.

What should I tell my healthcare provider before starting SABRIL?

If you or your child has CPS, before taking SABRIL tell your healthcare provider about all of your medical conditions, including if you or your child:

- have or had an allergic reaction to SABRIL, such as hives, itching, or trouble breathing.
- have or had any vision problems.
- have or had any kidney problems.
- have or had low red blood cell counts (anemia).
- have or had any nervous or mental illnesses such as depression, mood problems, thoughts of suicide, or attempts at suicide.
- are breastfeeding or planning to breastfeed. SABRIL can pass into breast milk and may harm your baby. Talk to your healthcare provider about the best way to feed your baby if you take SABRIL.
- are pregnant or plan to become pregnant. SABRIL can cause harm to your unborn baby. You and your healthcare provider will have to decide if you should take SABRIL while you are pregnant.

Pregnancy Registry:

If you become pregnant while taking SABRIL, talk to your healthcare provider about registering with the North American Antiepileptic Drug Pregnancy Registry. You can enroll in this registry by calling 1-888-233-2334. Information on the registry can also be found at the website http://www.aedpregnancyregistry.org/. The purpose of this registry is to collect information about the safety of antiepileptic medicine during pregnancy.

If you are a parent or caregiver whose baby has IS, before giving SABRIL to your baby, tell your healthcare provider about all of your baby’s medical conditions, including if your baby has or ever had:

- an allergic reaction to SABRIL, such as hives, itching, or trouble breathing.
- any vision problems.
- any kidney problems.

Tell your healthcare provider about all the medicines you or your child take, including prescription and over-the-counter medicines, vitamins, and herbal supplements. SABRIL and other medicines may affect each other causing side effects.

How should I take SABRIL?

- SABRIL comes as tablets or as packets containing powder for mixing with water to make an oral solution.
- You or your child will receive SABRIL from a specialty pharmacy.
- Take SABRIL exactly as your healthcare provider tells you to. SABRIL is usually taken 2 times each day.
- SABRIL may be taken with or without food.
- Before starting to take SABRIL, talk to your healthcare provider about what you or your child should do if a SABRIL dose is missed.
- If you or your child are taking SABRIL for CPS and the seizures do not improve enough within 3 months, your healthcare provider will stop prescribing SABRIL.
- If your child is taking SABRIL for IS and the seizures do not improve within 2 to 4 weeks, your healthcare provider will stop prescribing SABRIL.
- Do not stop taking SABRIL suddenly. This can cause serious problems. Stopping SABRIL or any seizure medicine suddenly can cause seizures that will not stop (status epilepticus) in people who are being treated for seizures. You should follow your healthcare provider’s instructions on how to stop taking SABRIL.
- Tell your healthcare provider right away about any increase in seizures when SABRIL treatment is being stopped. Before your child starts taking SABRIL, speak to your child’s healthcare provider about what to do if your baby misses a dose, vomits, spits up, or only takes part of the dose of SABRIL.
- Do not stop taking SABRIL without talking to your healthcare provider. If SABRIL improves your (or your child’s) seizures, you and your healthcare provider should talk about whether the benefit of taking SABRIL is more important than the risk of vision loss, and decide if you (or your child) will continue to take SABRIL.
- If you are giving SABRIL for oral solution to your child, it can be given at the same time as their meal. SABRIL powder should be mixed with water only.
- See “Instructions for Use” for detailed information about how to mix and give SABRIL for oral solution to your child the right way.

What should I avoid while taking SABRIL?

SABRIL causes sleepiness and tiredness. Adults taking SABRIL should not drive, operate machinery, or perform any hazardous task, unless you and your healthcare provider have decided that you can do these things safely.

What are the possible side effects of SABRIL?

SABRIL can cause serious side effects, including:

- See “What is the most important information I should know about SABRIL?”
- sleepiness and tiredness. See “What should I avoid while taking SABRIL?”
- SABRIL may cause your baby to be sleepy. Sleepy babies may have a harder time suckling and feeding, or may be irritable.
- weight gain that happens without swelling.

The following serious side effects happen in adults. It is not known if these side effects also happen in babies who take SABRIL.

- low red blood cell counts (anemia).
- nerve problems. Symptoms of a nerve problem can include numbness and tingling in your toes or feet. It is not known if nerve problems will go away after you stop taking SABRIL.
- swelling.

If you or your child has CPS, SABRIL may make certain types of seizures worse. Tell your healthcare provider right away if your (or your child's) seizures get worse.

The most common side effect of SABRIL in adults include blurred vision, sleepiness, dizziness, problems walking or feeling uncoordinated, shaking (tremor), and tiredness.

The most common side effect of SABRIL in children 3 to 16 years of age is weight gain. Also expect side effects like those seen in adults.

If you are giving SABRIL to your baby for IS:

SABRIL may make certain types of seizures worse. You should tell your baby’s healthcare provider right away if your baby’s seizures get worse. Tell your baby’s healthcare provider if you see any changes in your baby’s behavior.

The most common side effects of SABRIL in babies include:

- sleepiness - SABRIL may cause your baby to be sleepy. Sleepy babies may have a harder time suckling and feeding or may be irritable.
- swelling in the bronchial tubes (bronchitis)
- ear infection
- irritability

Tell your healthcare provider if you or your child have any side effect that bothers you or that does not go away. These are not all the possible side effects of SABRIL.

Call your doctor for medical advice about side effects. You may report side effects to FDA at 1-800-FDA-1088.

How should I store SABRIL?

- Store SABRIL tablets and SABRIL packets at room temperature between 68ºF to 77ºF (20ºC to 25ºC).

Keep SABRIL and all medicines out of the reach of children.

General information about the safe and effective use of SABRIL.

Medicines are sometimes prescribed for purposes other than those listed in a Medication Guide. You can ask your pharmacist or healthcare provider for information about SABRIL that is written for health professionals. Do not use SABRIL for a condition for which it was not prescribed. Do not give SABRIL to other people, even if they have the same symptoms that you have. It may harm them.

What are the ingredients in SABRIL?
Active Ingredient: vigabatrin
Inactive Ingredients:

- Tablets: hydroxypropyl methylcellulose, magnesium stearate, microcrystalline cellulose, polyethylene glycols, povidone, sodium starch glycolate, and titanium dioxide
- For oral solution: povidone

Marketed by: Lundbeck, Deerfield, IL 60015, U.S.A.

SABRIL is a registered trademark of Lundbeck

For more information, go to www.SABRIL.net or call 1-866-402-8520.

This Medication Guide has been approved by the U.S. Food and Drug Administration. Revised: 10/2021

INSTRUCTIONS FOR USE

SABRIL® (SAY-bril)

(vigabatrin)

for oral solution

Read this Instructions for Use before your child starts taking SABRIL and each time you get a refill. There may be new information. This information does not take the place of talking with your healthcare provider about your child’s medical condition or treatment. Talk to your healthcare provider if you have any questions about the right dose of medicine to give your child or how to mix it.

Important Note:

- SABRIL for oral solution comes in a packet
- Sabril packet contains 500 mg of powder
- SABRIL must be mixed with water only. The water may be cold or at room temperature.
- Your healthcare provider will tell you:
  - how many packets of SABRIL you will need for each dose
  - how many milliliters (mL) of water to use to mix one dose of SABRIL
  - how many milliliters (mL) of the powder and water mixture you will need for each dose of medicine
- SABRIL should be given right away after it is mixed
- Use the oral syringes, provided by the pharmacy, to measure and give the correct dose. Do not use a household teaspoon or tablespoon.

Supplies you will need to mix 1 dose of SABRIL:

- The number of packets of SABRIL needed for each dose
- 2 clean cups: 1 for mixing and 1 for water. The cup used for mixing SABRIL should be clear so you can see if the powder is dissolved
- Water to mix with the SABRIL powder
- One small 3 mL oral syringe and one large 10 mL oral syringe which are provided by the pharmacy
- Small spoon or other clean utensil to stir the mixture
- Scissors

Step 1: Start with 1 of the empty cups and the total number of packets you will need for 1 dose.

Step 2: Before you open the packet, tap it to settle all the powder to the bottom of the packet.

Step 3: Use a pair of scissors to cut open the SABRIL packet along the dotted line.

Step 4: Empty the entire contents of the SABRIL packet into 1 of the clean empty cups (see Figure A).

- Repeat steps 2 to 4 above to open all of the packets needed for 1 dose of SABRIL.

Step 5: Take the second cup and fill it half way with water (see Figure B).

Do not mix SABRIL with anything other than water.

- You will use the larger oral syringe (10 mL) to draw up the water needed to mix with the powder from the packets. You will need 10 mL of water for each packet of SABRIL.
  For example:
  - If you are using 1 packet of SABRIL, you will need to use 10 mL of water (fill the 10 mL oral syringe 1 time)
  - If you are using 2 packets of SABRIL, you will need to use 20 mL of water (fill the 10 mL oral syringe 2 times)
  - If you are using 3 packets of SABRIL, you will need to use 30 mL of water (fill the 10 mL oral syringe 3 times)

Step 6: Use the 10 mL oral syringe to draw up 10 mL of water. To do this, put the tip of the oral syringe all the way into the water in your cup. Then pull the plunger up towards you until the edge of the plunger is at the 10 mL line on the barrel of the oral syringe (see Figure C).

- If you see bubbles of air in the oral syringe after drawing up the water, turn the oral syringe so the tip is pointing up (see Figure D). The air will move to the top of the oral syringe. Pull the plunger back towards you and then push it back gently into the oral syringe to get rid of the bubbles. Tiny bubbles are normal.

Step 7: Check the oral syringe to make sure it is filled with water up to the 10 mL line (see Figure E).

Step 8: Get the second cup that contains the SABRIL needed for your dose.

Step 9: Hold the 10mL oral syringe that is filled with water with the tip pointing down over the SABRIL.

Step 10: Slowly push the oral syringe plunger all the way down to empty the water from the oral syringe straight into the cup containing the SABRIL (see Figure F).

Repeat steps 6 through 10 until all of the water that is needed to mix 1 dose of SABRIL has been added to the cup containing the powder.

Step 11: Stir the mixture with the small spoon or other clean utensil until the solution is clear (see Figure G). This means that all of the powder is dissolved and ready for use.

- To give a dose of SABRIL to your child, you should use the oral syringe to draw up the total number of mLs of the mixture that your healthcare provider tells you to.
  - If you are giving 3 mL or less of the mixture, use the smaller 3 mL oral syringe.
  - If you are giving more than 3 mL of the mixture, use the larger 10 mL oral syringe (this is the oral syringe that you just used to add the water).

Step 12: Put the tip of the oral syringe all the way into the mixture. Pull the plunger up towards you to draw up the mixture. Stop when the edge of the plunger lines up with markings on the barrel of the oral syringe that matches the number of mLs of mixture your healthcare provider told you to give (see Figure H).

- If you see bubbles of air in the oral syringe after drawing up the mixture, turn the oral syringe so the tip is pointing up (see Figure I). The air will move to the top of the oral syringe. Pull the plunger back towards you and then gently push it back in the oral syringe in order to get rid of the bubbles. Tiny bubbles are normal.

Step 13: Place the tip of the oral syringe into your child’s mouth and point the oral syringe towards either cheek (see Figure J). Push on the plunger slowly, a small amount at a time, until all of the mixture in the oral syringe is given.

- If the dose you are giving your child is more than 10 mLs, repeat steps 12 and 13 until you give the total dose of mixture prescribed by your healthcare provider.

Step 14: Throw away any mixture that is left over. Do not save or reuse any leftover mixture.

Step 15: Wash the oral syringes and mixing cups in warm water. To clean the oral syringes, remove the plunger by gently pulling it straight out of the barrel. The barrel and plunger can be hand washed with soap and water, rinsed, and allowed to dry.

This Instructions for Use has been approved by the U.S. Food and Drug Administration.

Marketed by: Lundbeck, Deerfield, IL 60015, U.S.A.

SABRIL is a registered trademark of Lundbeck

Revised: 10/2021

PACKAGE LABEL

PRINCIPAL DISPLAY PANEL
NDC 67386-211-65
Sabril®
(vigabatrin) for Oral Solution
500 mg
DISPENSE THE ENCLOSED MEDICATION
GUIDE WITH EACH PRESCRIPTION.
Rx only
50 Packets

500 mg